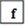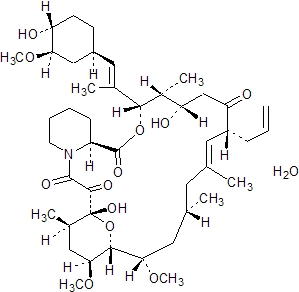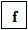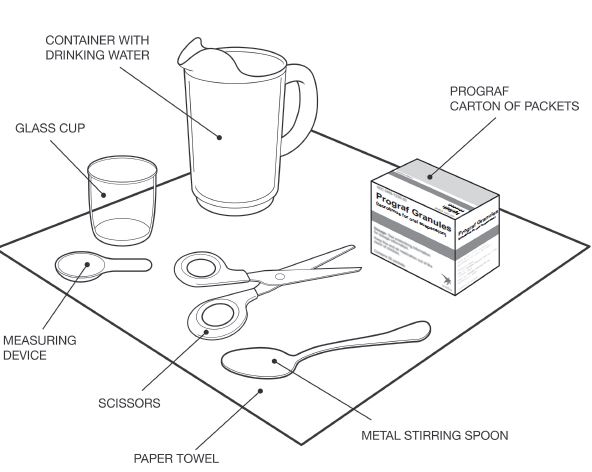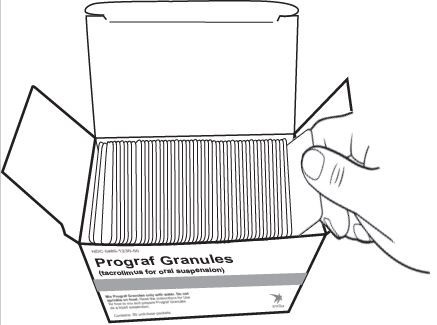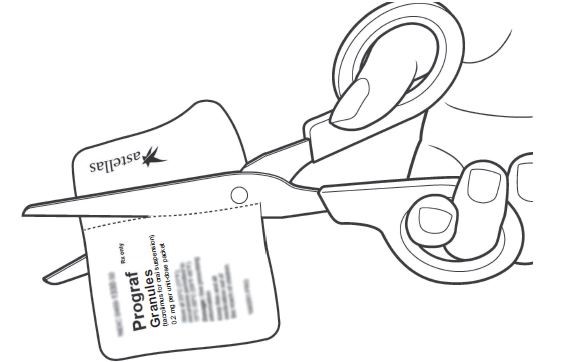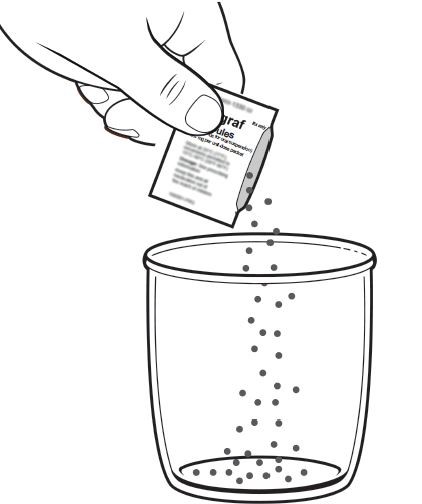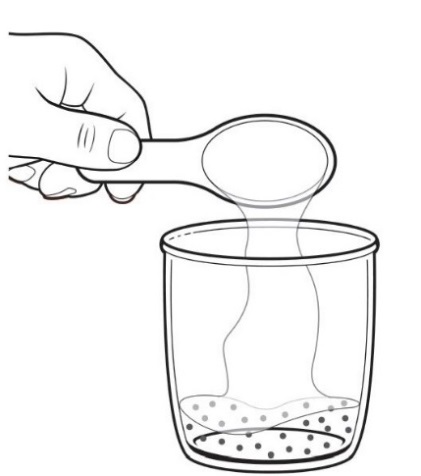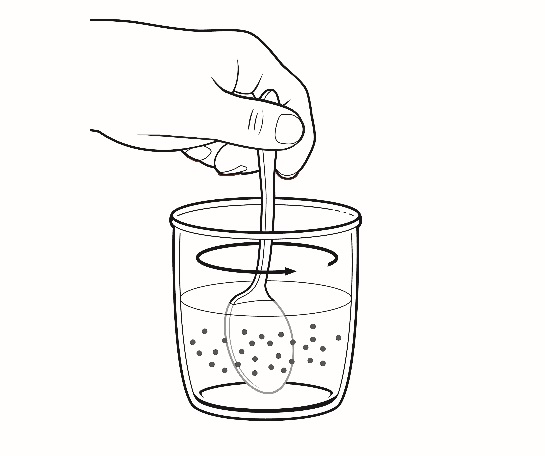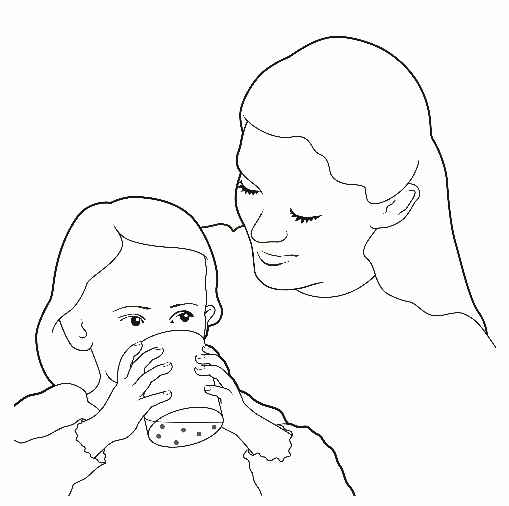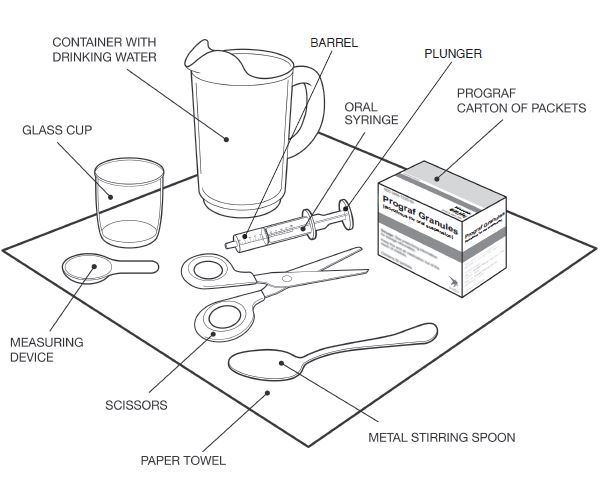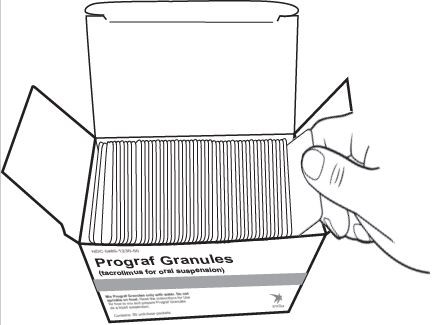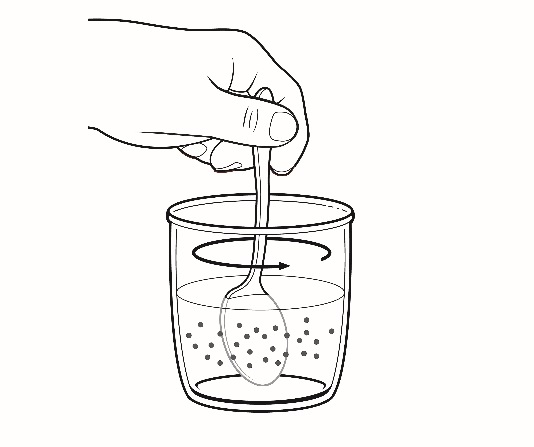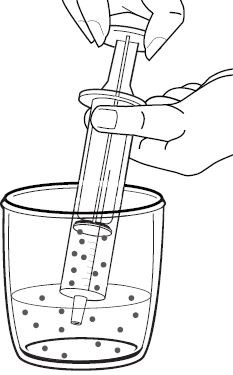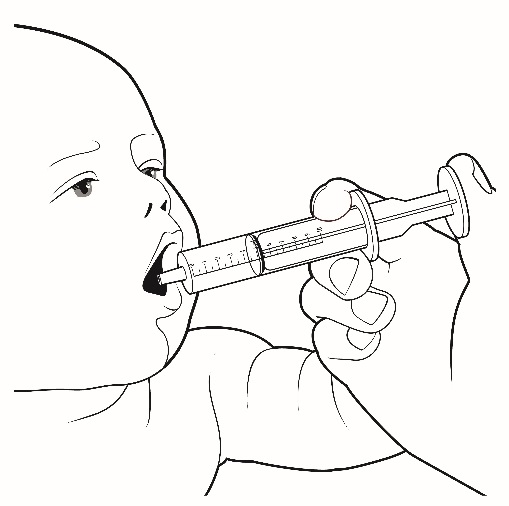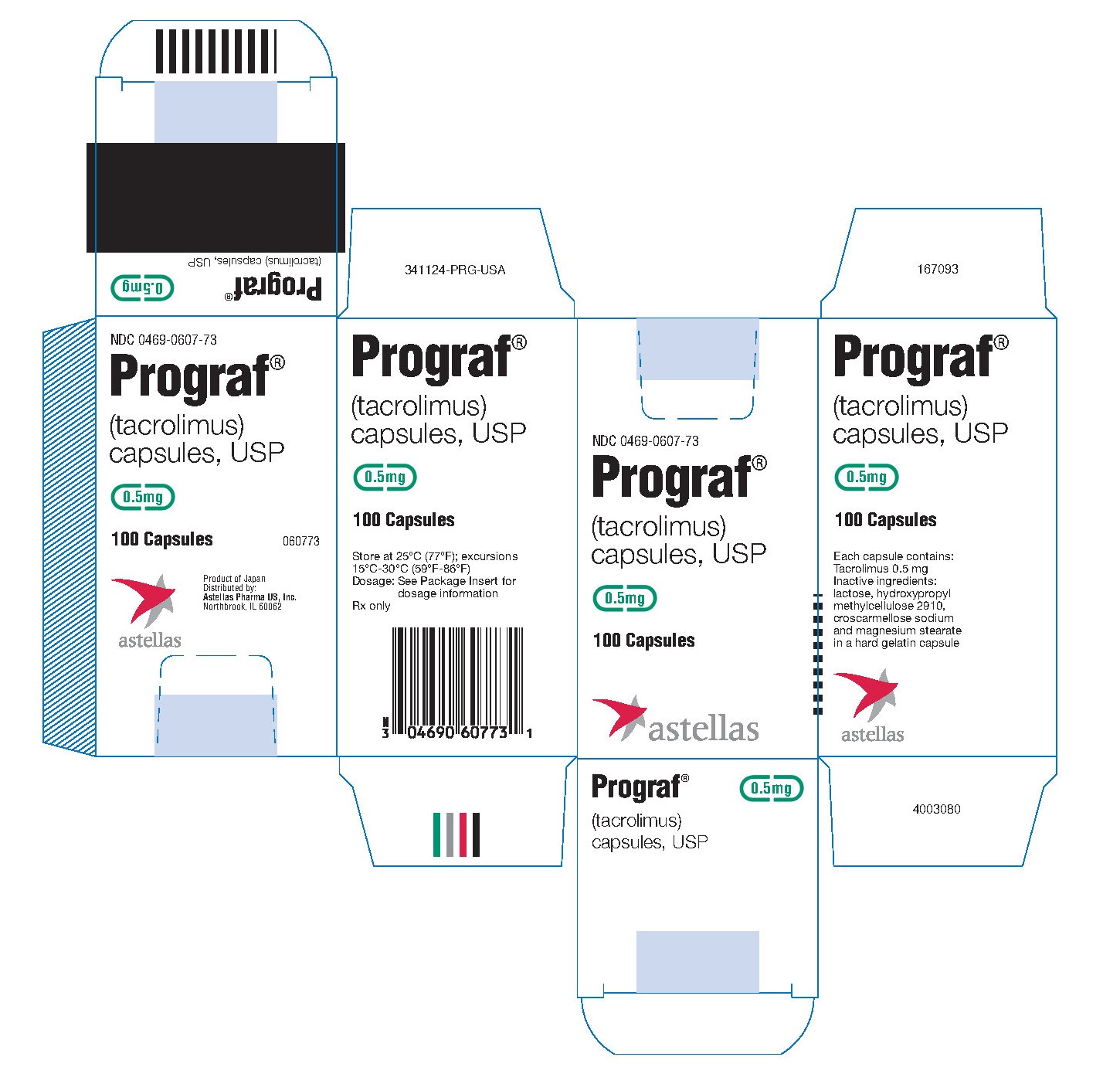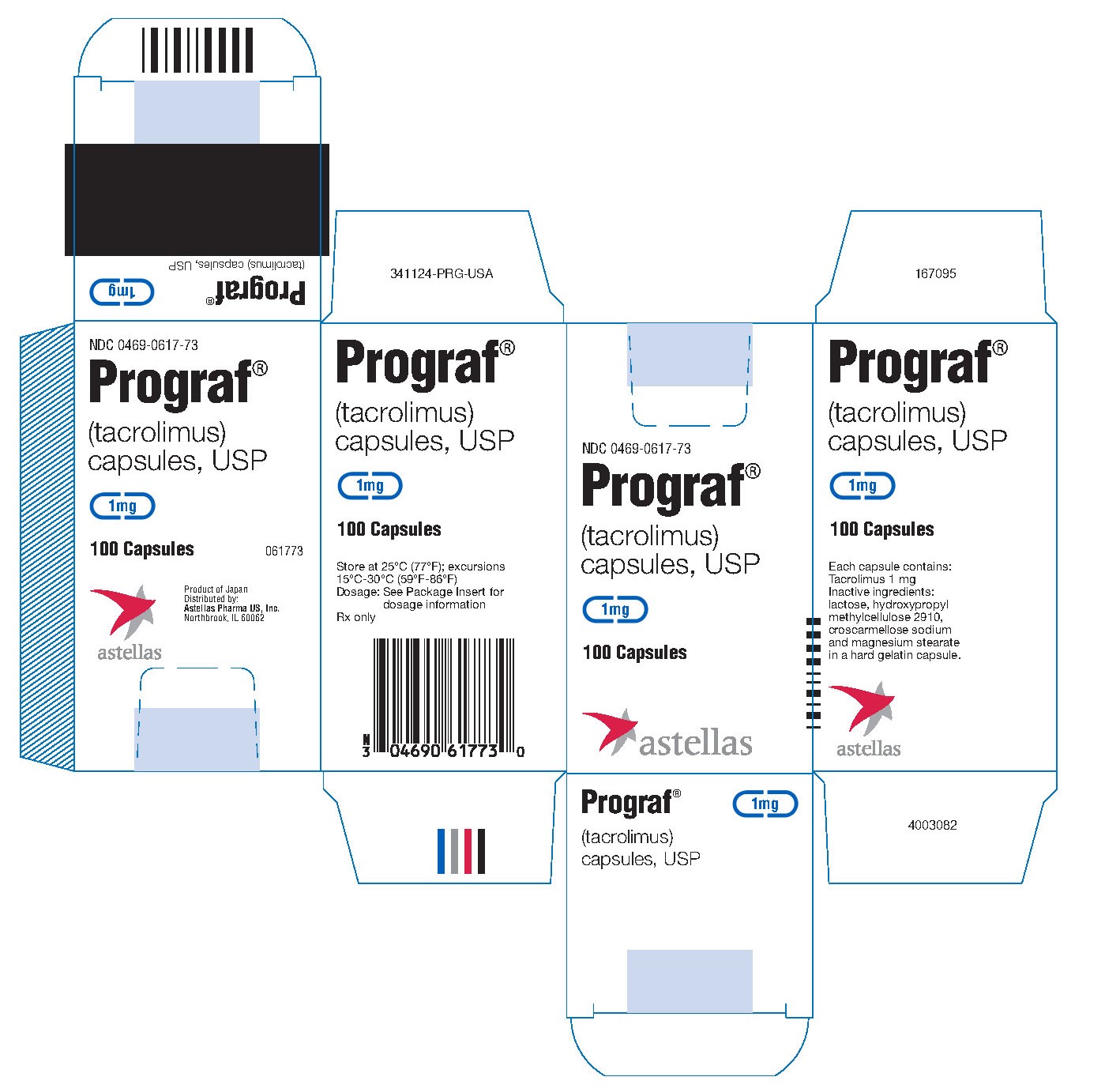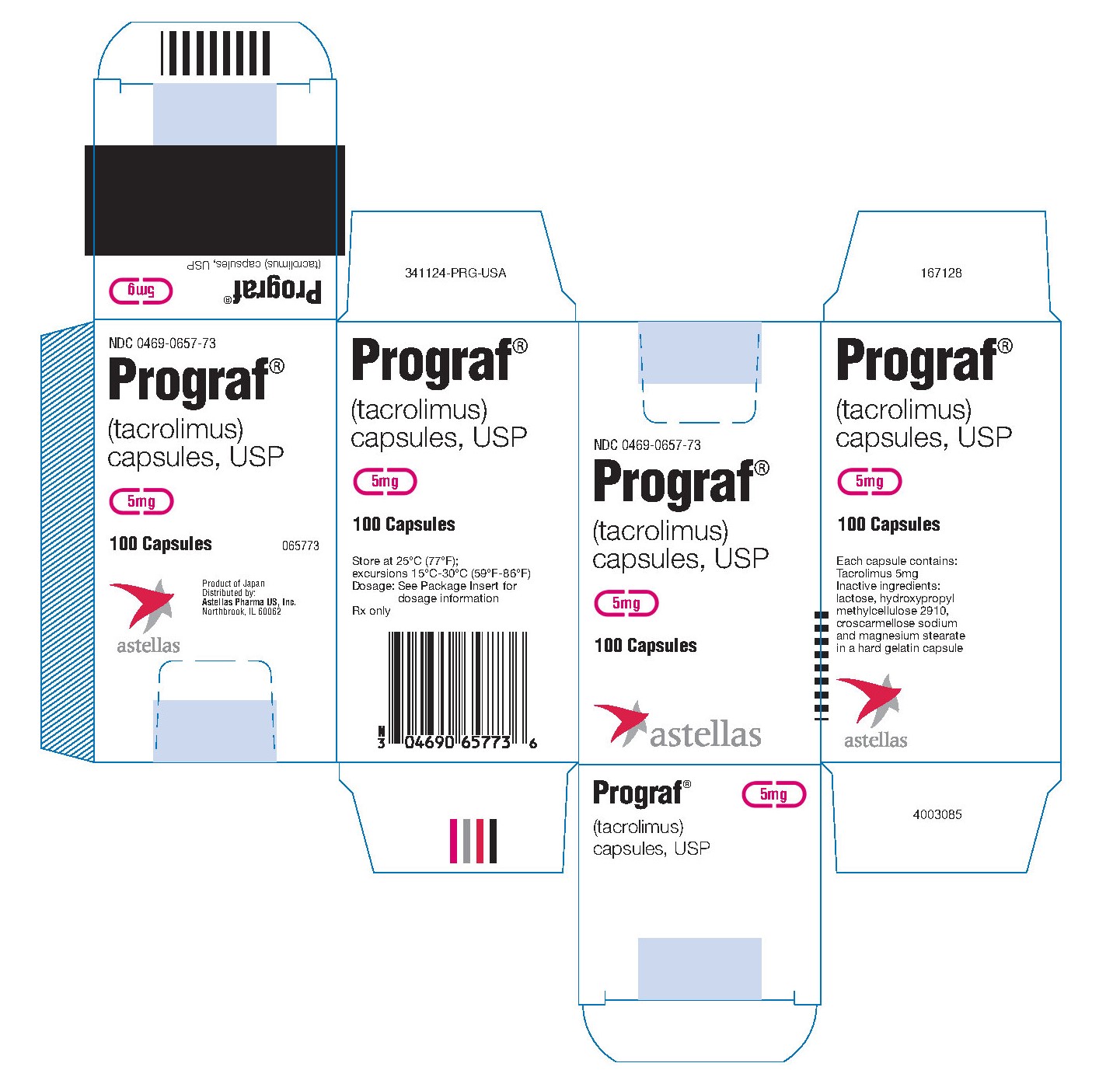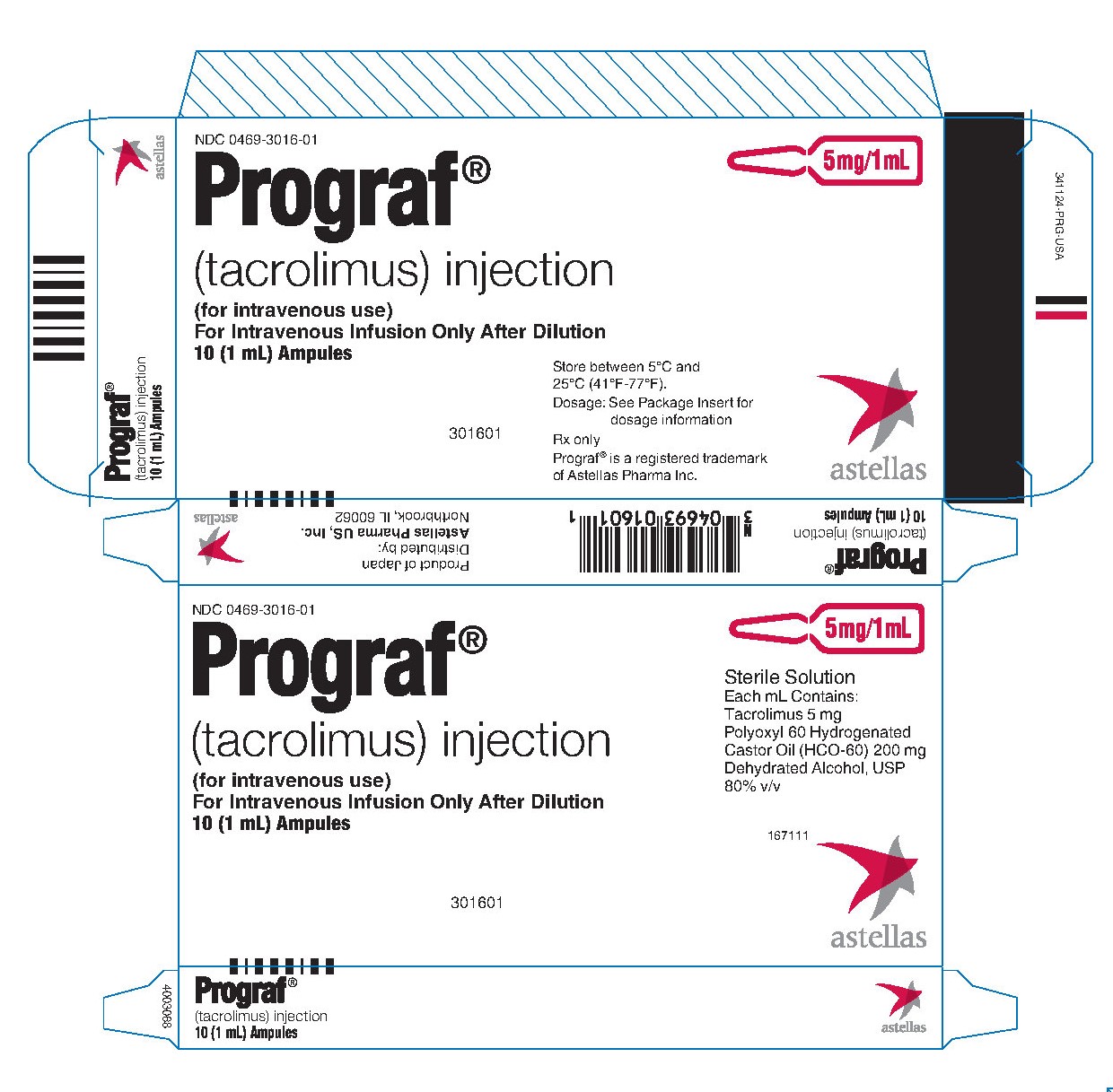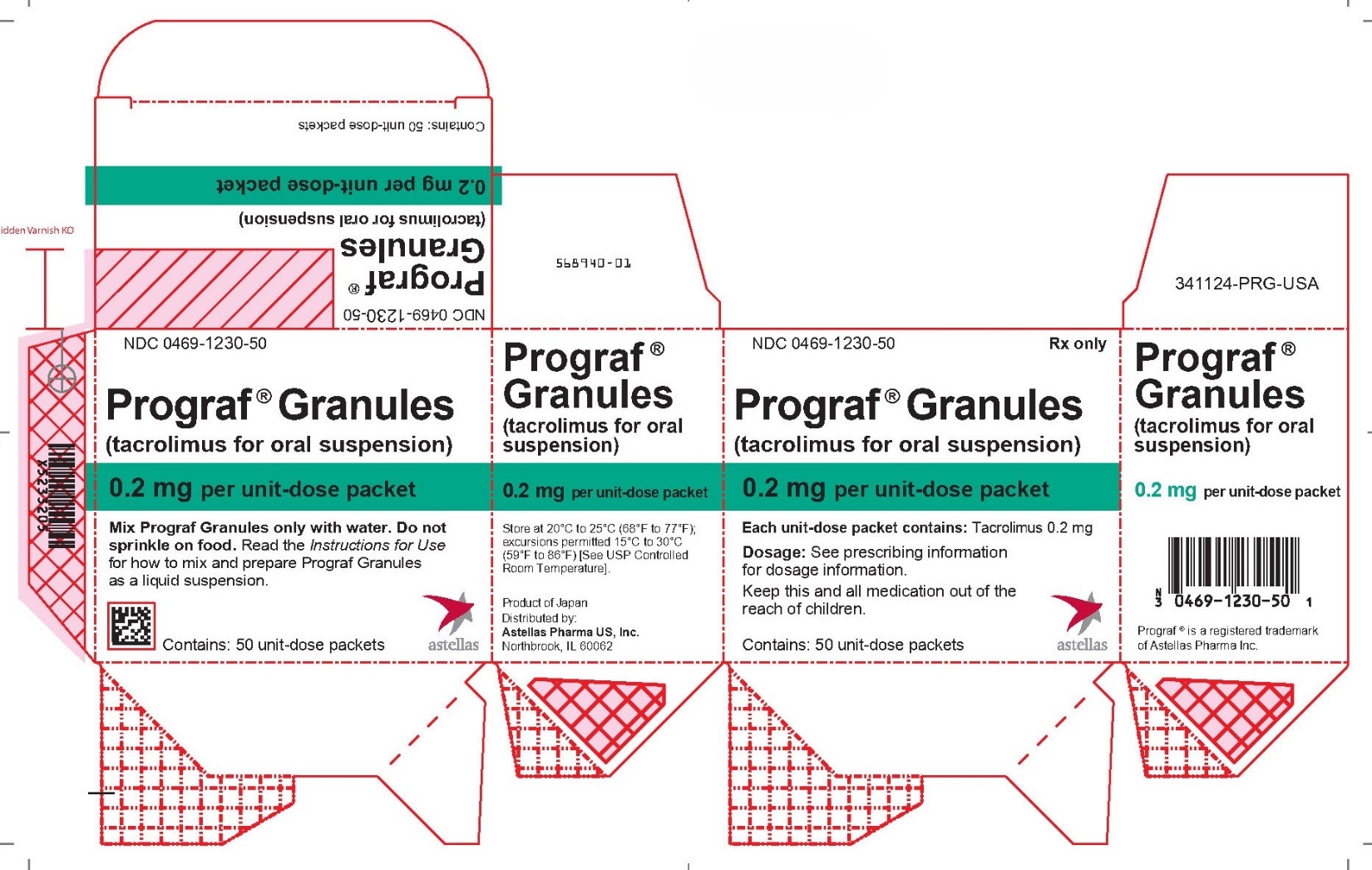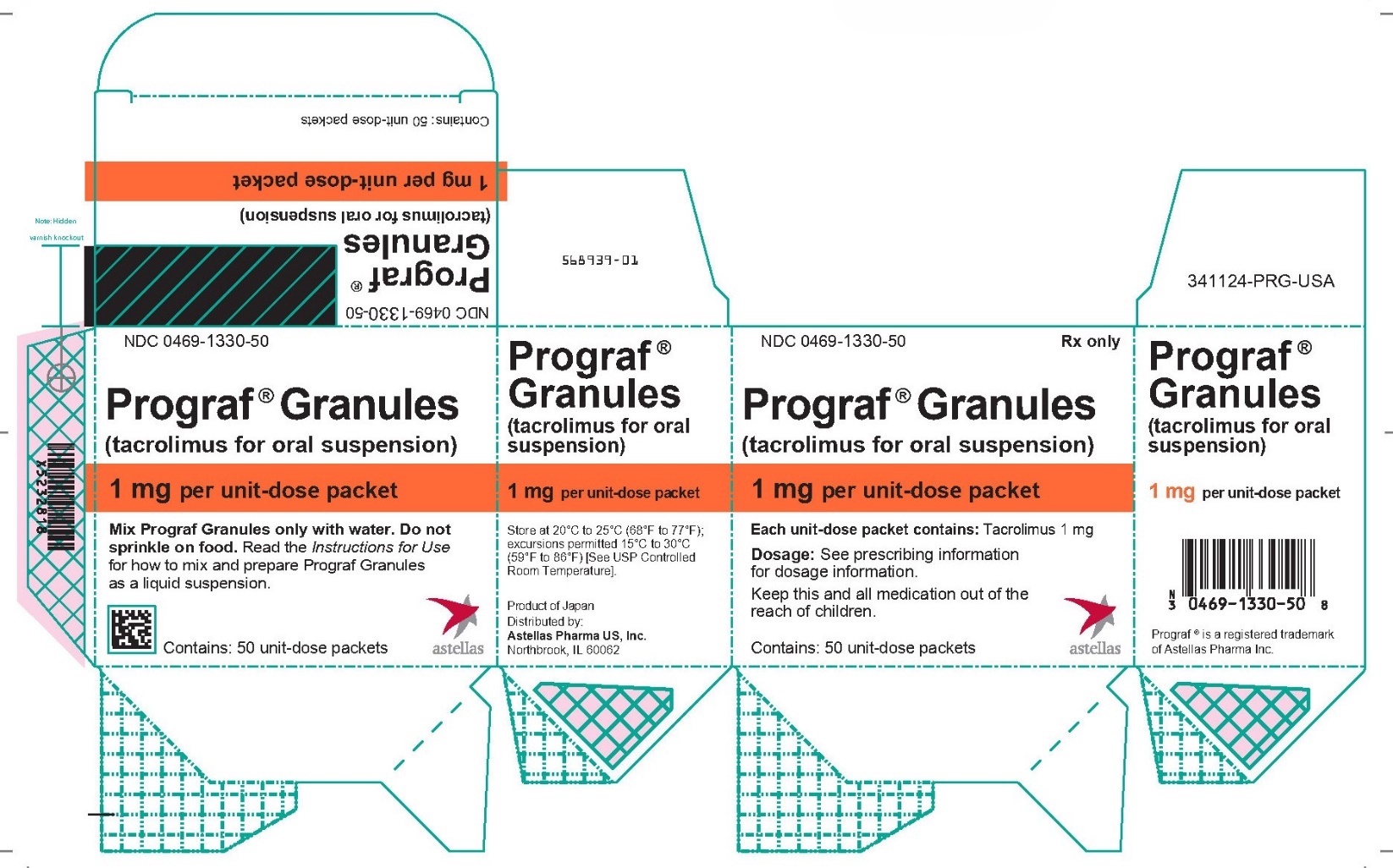 DRUG LABEL: Prograf
NDC: 0469-0607 | Form: CAPSULE, GELATIN COATED
Manufacturer: Astellas Pharma US, Inc.
Category: prescription | Type: HUMAN PRESCRIPTION DRUG LABEL
Date: 20230825

ACTIVE INGREDIENTS: TACROLIMUS 0.5 mg/1 1

HIGHLIGHTS OF PRESCRIBING INFORMATION

These highlights do not include all the information needed to use PROGRAF® safely and effectively. See full prescribing information for PROGRAF.
PROGRAF (tacrolimus) capsules, for oral use
PROGRAF (tacrolimus) injection, for intravenous use
PROGRAF Granules (tacrolimus for oral suspension)
Initial U.S. Approval: 1994

RECENT MAJOR CHANGES

Warnings and Precautions (5.5, 5.10, 5.16) 11/2022

Warnings and Precautions, Cannabidiol Drug Interactions (5.17) 08/2023

WARNING: MALIGNANCIES AND SERIOUS INFECTIONS

See full prescribing information for complete boxed warning.

Increased risk for developing serious infections and malignancies with PROGRAF or other immunosuppressants that may lead to hospitalization or death. (5.1, 5.2)

1 INDICATIONS AND USAGE

PROGRAF is a calcineurin-inhibitor immunosuppressant indicated for the prophylaxis of organ rejection in adult and pediatric patients receiving allogeneic liver, kidney, heart, or lung transplants, in combination with other immunosuppressants. (1.1)

2 DOSAGE AND ADMINISTRATION

- Intravenous (IV) use recommended for patients who cannot tolerate oral formulations (capsules or suspension). (2.1, 2.2)
- Administer capsules or suspension consistently with or without food. (2.1)
- Therapeutic drug monitoring is recommended. (2.1, 2.6)
- Avoid eating grapefruit or drinking grapefruit juice. (2.1)
- See dosage adjustments for African-American patients (2.2), hepatic and renal impaired. (2.4, 2.5)
- For complete dosing information, see Full Prescribing Information.

ADULT
Patient Population | Initial Oral Dosage (formulation) | Whole Blood Trough Concentration Range
Kidney Transplant
With azathioprine | 0.2 mg/kg/day capsules, divided in two doses, every 12 hours | Month 1-3: 7-20 ng/mL Month 4-12: 5-15 ng/mL
With MMF/IL-2 receptor antagonist | 0.1 mg/kg/day capsules, divided in two doses, every 12 hours | Month 1-12: 4-11 ng/mL
Liver Transplant
With corticosteroids only | 0.1-0.15 mg/kg/day capsules, divided in two doses, every 12 hours | Month 1-12: 5-20 ng/mL
Heart Transplant
With azathioprine or MMF | 0.075 mg/kg/day capsules, divided in two doses, every 12 hours | Month 1-3: 10-20 ng/mL Month ≥ 4: 5-15 ng/mL
Lung Transplant
With azathioprine or MMF | 0.075 mg/kg/day [Patients with cystic fibrosis may require higher doses due to lower bioavailability.] capsules, divided in two doses, every 12 hours | Month 1-3: 10-15 ng/mL Month 4-12: 8-12 ng/mL
PEDIATRIC
Patient Population | Initial Oral Dosage (formulation) | Whole Blood Trough Concentration Range
Kidney Transplant
 | 0.3 mg/kg/day capsules or oral suspension, divided in two doses, every 12 hours | Month 1-12: 5-20 ng/mL
Liver Transplant
 | 0.15-0.2 mg/kg/day capsules or 0.2 mg/kg/day oral suspension, divided in two doses, every 12 hours | Month 1-12: 5-20 ng/mL
Heart Transplant
 | 0.3 mg/kg/day [Dose at 0.1 mg/kg/day if antibody induction treatment is administered.] capsules or oral suspension, divided in two doses, every 12 hours | Month 1-12: 5-20 ng/mL
Lung Transplant
 | 0.3 mg/kg/day, capsules or oral suspension, divided in two doses, every 12 hours | Weeks 1-2: 10-20 ng/mL Week 2 to Month 12: 10-15 ng/mL
MMF= Mycophenolate mofetil

3 DOSAGE FORMS AND STRENGTHS

- Capsules: 0.5 mg, 1 mg and 5 mg (3)
- Injection: 5 mg/mL (3)
- For oral suspension: 0.2 mg, 1 mg unit-dose packets containing granules (3)

4 CONTRAINDICATIONS

- Hypersensitivity to tacrolimus or HCO-60 (polyoxyl 60 hydrogenated castor oil). (4)

5 WARNINGS AND PRECAUTIONS

- Not Interchangeable with Extended-Release Tacrolimus Products - Medication Errors: Instruct patients or caregivers to recognize the appearance of PROGRAF capsules. (5.3)
- New Onset Diabetes After Transplant: Monitor blood glucose. (5.4)
- Nephrotoxicity (acute and/or chronic): Reduce the dose; use caution with other nephrotoxic drugs. (5.5)
- Neurotoxicity: Including risk of Posterior Reversible Encephalopathy Syndrome (PRES); monitor for neurologic abnormalities; reduce or discontinue PROGRAF. (5.6)
- Hyperkalemia: Monitor serum potassium levels. Consider carefully before using with other agents also associated with hyperkalemia. (5.7)
- Hypertension: May require antihypertensive therapy. Monitor relevant drug-drug interactions. (5.8)
- Anaphylactic Reactions with IV formulation: Observe patients receiving PROGRAF injection for signs and symptoms of anaphylaxis. (5.9)
- Not recommended for use with sirolimus: Not recommended in liver and heart transplant due to increased risk of serious adverse reactions. (5.10)
- Myocardial Hypertrophy: Consider dose reduction/discontinuation. (5.13)
- Immunizations: Avoid live vaccines. (5.14)
- Pure Red Cell Aplasia: Consider discontinuation of PROGRAF. (5.15)
- Thrombotic Microangiopathy, Including Hemolytic Uremic Syndrome and Thrombotic Thrombocytopenic Purpura: May occur, especially in patients with infections and certain concomitant medications. (5.16)

6 ADVERSE REACTIONS

The most common adverse reactions (≥ 15%) were abnormal renal function, hypertension, diabetes mellitus, fever, CMV infection, tremor, hyperglycemia, leukopenia, infection, anemia, bronchitis, pericardial effusion, urinary tract infection, constipation, diarrhea, headache, abdominal pain, insomnia, paresthesia, peripheral edema, nausea, hyperkalemia, hypomagnesemia, and hyperlipemia. (6.1)

To report SUSPECTED ADVERSE REACTIONS, contact Astellas Pharma US, Inc. at 1-800-727-7003 or FDA at 1-800-FDA-1088 or www.fda.gov/medwatch.

7 DRUG INTERACTIONS

- Mycophenolic Acid Products: Can increase MPA exposure after crossover from cyclosporine to PROGRAF; monitor for MPA-related adverse reactions and adjust MMF or MPA dose as needed. (7.1)
- Nelfinavir and Grapefruit Juice: Increased tacrolimus concentrations via CYP3A inhibition; avoid concomitant use. (7.2)
- CYP3A Inhibitors: Increased tacrolimus concentrations; monitor concentrations and adjust tacrolimus dose as needed. (5.11, 7.2)
- CYP3A4 Inducers: Decreased tacrolimus concentrations; monitor concentrations and adjust tacrolimus dose as needed. (5.11, 7.2)
- Therapeutic drug monitoring and dose reduction for PROGRAF should be considered when PROGRAF is co-administered with cannabidiol (5.17, 7.3).

8 USE IN SPECIFIC POPULATIONS

Pregnancy: Can cause fetal harm. Advise pregnant women of the potential risk to the fetus. (8.1, 8.3)

FULL PRESCRIBING INFORMATION

WARNING: MALIGNANCIES AND SERIOUS INFECTIONS

Increased risk for developing serious infections and malignancies with PROGRAF or other immunosuppressants that may lead to hospitalization or death. (5.1, 5.2)

1 INDICATIONS AND USAGE

1.1 Prophylaxis of Organ Rejection in Kidney, Liver, Heart, or Lung Transplant

PROGRAF® is indicated for the prophylaxis of organ rejection, in adult and pediatric patients receiving allogeneic kidney transplant [see Clinical Studies (14.1)], liver transplant [see Clinical Studies (14.2)], heart transplant [see Clinical Studies (14.3)], or lung transplant [see Clinical Studies (14.4)] in combination with other immunosuppressants.

2 DOSAGE AND ADMINISTRATION

2.1 Important Administration Instructions

PROGRAF should not be used without supervision by a physician with experience in immunosuppressive therapy.

PROGRAF capsules and PROGRAF Granules are not interchangeable or substitutable for other tacrolimus extended-release products. This is because rate of absorption following the administration of an extended-release tacrolimus product is not equivalent to that of an immediate-release tacrolimus drug product. Under- or overexposure to tacrolimus may result in graft rejection or other serious adverse reactions. Changes between tacrolimus immediate-release and extended- release dosage forms must occur under physician supervision [see Warnings and Precautions (5.3)].

Intravenous Formulation - Administration Precautions due to Risk of Anaphylaxis

Intravenous use is recommended for patients who cannot tolerate oral formulations, and conversion from intravenous to oral PROGRAF is recommended as soon as oral therapy can be tolerated to minimize the risk of anaphylactic reactions that occurred with injectables containing castor oil derivatives [see Warnings and Precautions (5.9)].

Patients receiving PROGRAF injection should be under continuous observation for at least the first 30 minutes following the start of the infusion and at frequent intervals thereafter. If signs or symptoms of anaphylaxis occur, the infusion should be stopped. An aqueous solution of epinephrine should be available at the bedside as well as a source of oxygen.

Oral Formulations (Capsules and Oral Suspension)

If patients are able to initiate oral therapy, the recommended starting doses should be initiated. PROGRAF Granules for oral suspension or PROGRAF capsules may be taken with or without food. However, since the presence of food affects the bioavailability of PROGRAF, if taken with food, it should be taken consistently the same way each time [see Clinical Pharmacology (12.3)].

General Administration Instructions

Patients should not eat grapefruit or drink grapefruit juice in combination with PROGRAF [see Drug Interactions (7.2)].

PROGRAF should not be used simultaneously with cyclosporine. PROGRAF or cyclosporine should be discontinued at least 24 hours before initiating the other. In the presence of elevated PROGRAF or cyclosporine concentrations, dosing with the other drug usually should be further delayed.

Therapeutic drug monitoring (TDM) is recommended for all patients receiving PROGRAF [see Dosage and Administration (2.6)].

2.2 Dosage Recommendations for Adult Kidney, Liver, Heart, or Lung Transplant Patients - Capsules and Injection

Capsules

If patients are able to tolerate oral therapy, the recommended oral starting doses should be initiated. The initial dose of PROGRAF capsules should be administered no sooner than 6 hours after transplantation in the liver, heart, or lung transplant patients. In kidney transplant patients, the initial dose of PROGRAF capsules may be administered within 24 hours of transplantation, but should be delayed until renal function has recovered.

The initial oral PROGRAF capsule dosage recommendations for adult patients with kidney, liver, heart, or lung transplants and whole blood trough concentration range are shown in Table 1. Perform therapeutic drug monitoring (TDM) to ensure that patients are within the ranges listed in Table 1.

Table 1. Summary of Initial Oral PROGRAF Capsules Dosage Recommendations and Whole Blood Trough Concentration Range in Adults
Patient Population | PROGRAF Capsules [African-American patients may require higher doses compared to Caucasians (see Table 2).] Initial Oral Dosage | Whole Blood Trough Concentration Range
Kidney Transplant
With Azathioprine | 0.2 mg/kg/day, divided in two doses, administered every 12 hours | Month 1-3: 7-20 ng/mL; Month 4-12: 5-15 ng/mL
With MMF/IL-2 receptor antagonist [In a second smaller trial, the initial dose of tacrolimus was 0.15-0.2 mg/kg/day and observed tacrolimus concentrations were 6-16 ng/mL. during month 1-3 and 5-12 ng/mL during month 4-12 [see Clinical Studies (14.1)].] | 0.1 mg/kg/day, divided in two doses, administered every 12 hours | Month 1-12: 4-11 ng/mL
Liver Transplant
With corticosteroids only | 0.10-0.15 mg/kg/day, divided in two doses, administered every 12 hours | Month 1-12: 5-20 ng/mL
Heart Transplant
With azathioprine or MMF | 0.075 mg/kg/day, divided in two doses, administered every 12 hours | Month 1-3: 10-20 ng/mL; Month ≥ 4: 5-15 ng/mL
Lung Transplant
With azathioprine or MMF | 0.075 mg/kg/day [Patients with cystic fibrosis may require higher doses due to lower bioavailability [see Clinical Pharmacology (12.3)].] , divided in two doses, administered every 12 hours | Month 1-3: 10-15 ng/mL; Month 4-12: 8-12 ng/mL

Dosage should be titrated based on clinical assessments of rejection and tolerability. PROGRAF dosages lower than the recommended initial dosage may be sufficient as maintenance therapy. Adjunct therapy with adrenal corticosteroids is recommended early post-transplant.

The data in kidney transplant patients indicate that the African-American patients required a higher dose to attain comparable trough concentrations compared to Caucasian patients (Table 2) [see Use in Specific Populations (8.8) and Clinical Pharmacology (12.3)].

Table 2. Comparative Dose and Trough Concentrations Based on Race
Time After Transplant | Caucasian; N = 114 |  | African-American; N = 56
Time After Transplant | Dose; (mg/kg) | Trough Concentrations; (ng/mL) | Dose; (mg/kg) | Trough Concentrations (ng/mL)
Day 7 | 0.18 | 12.0 | 0.23 | 10.9
Month 1 | 0.17 | 12.8 | 0.26 | 12.9
Month 6 | 0.14 | 11.8 | 0.24 | 11.5
Month 12 | 0.13 | 10.1 | 0.19 | 11.0

In lung transplantation, cystic fibrosis patients may have a reduced bioavailability of orally administered tacrolimus resulting in the need for higher doses to achieve target tacrolimus trough concentrations. Monitor tacrolimus trough concentrations and adjust the dose accordingly.

Intravenous Injection

PROGRAF injection should be used only as a continuous intravenous infusion and should be discontinued as soon as the patient can tolerate oral administration. The first dose of PROGRAF capsules should be given 8-12 hours after discontinuing the intravenous infusion.

The recommended starting dose of PROGRAF injection is 0.03-0.05 mg/kg/day in kidney or liver transplant, 0.01 mg/kg/day in heart transplant, and 0.01-0.03 mg/kg/day in lung transplant, given as a continuous intravenous infusion. Adult patients should receive doses at the lower end of the dosing range. Concomitant adrenal corticosteroid therapy is recommended early post-transplantation.

The whole blood trough concentration range described in Table 1 pertains to oral administration of PROGRAF only; while monitoring PROGRAF concentrations in patients receiving PROGRAF injection as a continuous intravenous infusion may have some utility, the observed concentrations will not represent comparable exposures to those estimated by the trough concentrations observed in patients on oral therapy.

Anaphylactic reactions have occurred with injectables containing castor oil derivatives, such as PROGRAF injection. Therefore, monitoring for signs and symptoms of anaphylaxis is recommended [see Warnings and Precautions (5.9)].

2.3 Dosage Recommendations for Pediatric Kidney, Liver, Heart, or Lung Transplant Patients

Oral formulations (capsules or oral suspension)

Pediatric patients, in general, need higher tacrolimus doses compared to adults: the higher dose requirements may decrease as the child grows older. Recommendations for the initial oral dosage for pediatric transplant patients and whole blood trough concentration range are shown in Table 3. Perform TDM to ensure that patients are within the ranges listed in Table 3.

Table 3. Summary of Initial PROGRAF Capsule and PROGRAF Granules Dosage Recommendations and Whole Blood Trough Concentration Range in Children
Patient Population | Initial PROGRAF Capsule and PROGRAF Granules Dosing | Whole Blood Trough Concentration Range
Pediatric kidney transplant patients [See Clinical Pharmacology (12.3), PROGRAF Granules Pharmacokinetics in Pediatric Patients.] | 0.3 mg/kg/day capsules or oral suspension, divided in two doses, administered every 12 hours | Month 1-12: 5-20 ng/mL
Pediatric liver transplant patients [See Clinical Studies (14.2), Liver Transplantation.] | 0.15-0.2 mg/kg/day capsules or 0.2 mg/kg/day oral suspension, divided in two doses, administered every 12 hours | Month 1-12: 5-20 ng/mL
Pediatric heart transplant patients | 0.3 mg/kg/day [Dose at 0.1 mg/kg/day if antibody induction treatment is administered.] capsules or oral suspension, divided in two doses, administered every 12 hours | Month 1-12: 5-20 ng/mL
Pediatric lung transplant patients | 0.3 mg/kg/day, [Patients with cystic fibrosis may require higher doses due to lower bioavailability [see Clinical Pharmacology (12.3)].] capsules or oral suspension, divided in two doses, administered every 12 hours | Week 1-2: 10-20 ng/mL; Week 2 to Month 12: 10-15 ng/mL

In lung transplantation, cystic fibrosis patients may have a reduced bioavailability of orally administered tacrolimus resulting in the need for higher doses to achieve target tacrolimus trough concentrations. Monitor tacrolimus trough concentrations and adjust the dose accordingly.

For conversion of pediatric patients from PROGRAF Granules to PROGRAF capsules or from PROGRAF capsules to PROGRAF Granules, the total daily dose should remain the same. Following conversion from one formulation to another formulation of tacrolimus, therapeutic drug monitoring is recommended [see Dosage and Administration (2.6)].

Intravenous Injection

If a patient is unable to receive an oral formulation, the patient may be started on PROGRAF injection. For pediatric liver transplant patients, the intravenous dose is 0.03-0.05 mg/kg/day.

2.4 Dosage Modification for Patients with Renal Impairment

Due to its potential for nephrotoxicity, consider dosing PROGRAF at the lower end of the therapeutic dosing range in patients who have received a liver, heart, or lung transplant, and have pre-existing renal impairment. Further reductions in dose below the targeted range may be required.

In kidney transplant patients with post-operative oliguria, the initial dose of PROGRAF should be administered no sooner than 6 hours and within 24 hours of transplantation, but may be delayed until renal function shows evidence of recovery [see Dosage and Administration (2.2), Warnings and Precautions (5.5), Use in Specific Populations (8.6), and Clinical Pharmacology (12.3)].

2.5 Dosage Modification for Patients with Hepatic Impairment

Due to the reduced clearance and prolonged half-life, patients with severe hepatic impairment (Child-Pugh ≥ 10) may require lower doses of PROGRAF. Close monitoring of blood concentrations is warranted.

The use of PROGRAF in liver transplant recipients experiencing post-transplant hepatic impairment may be associated with increased risk of developing renal insufficiency related to high whole blood concentrations of tacrolimus. These patients should be monitored closely, and dosage adjustments should be considered. Some evidence suggests that lower doses should be used in these patients [see Dosage and Administration (2.2), Warnings and Precautions (5.5), Use in Specific Populations (8.7), and Clinical Pharmacology (12.3)].

2.6 Therapeutic Drug Monitoring

Monitoring of tacrolimus blood concentrations in conjunction with other laboratory and clinical parameters is considered an essential aid to patient management for the evaluation of rejection, toxicity, dose adjustments, and compliance. Whole blood trough concentration range can be found in Table 1.

Factors influencing frequency of monitoring include but are not limited to hepatic or renal dysfunction, the addition or discontinuation of potentially interacting drugs and the post-transplant time. Blood concentration monitoring is not a replacement for renal and liver function monitoring and tissue biopsies. Data from clinical trials show that tacrolimus whole blood concentrations were most variable during the first week post-transplantation.

The relative risks of toxicity and efficacy failure are related to tacrolimus whole blood trough concentrations. Therefore, monitoring of whole blood trough concentrations is recommended to assist in the clinical evaluation of toxicity and efficacy failure.

Methods commonly used for the assay of tacrolimus include high-performance liquid chromatography with tandem mass spectrometric detection (HPLC/MS/MS) and immunoassays. Immunoassays may react with metabolites as well as parent compound. Therefore, assay results obtained with immunoassays may have a positive bias relative to results of HPLC/MS. The bias may depend upon the specific assay and laboratory. Comparison of the concentrations in published literature to patient concentrations using the current assays must be made with detailed knowledge of the assay methods and biological matrices employed. Whole blood is the matrix of choice and specimens should be collected into tubes containing ethylene diamine tetraacetic acid (EDTA) anticoagulant. Heparin anticoagulation is not recommended because of the tendency to form clots on storage. Samples which are not analyzed immediately should be stored at room temperature or in a refrigerator and assayed within 7 days; see assay instructions for specifics. If samples are to be kept longer, they should be deep frozen at -20°C. One study showed drug recovery > 90% for samples stored at -20°C for 6 months, with reduced recovery observed after 6 months.

2.7 Preparation and Administration Instructions of PROGRAF Injection for Pharmacists

Tacrolimus can cause fetal harm. Follow applicable special handling and disposal procedures^1 [see How Supplied/ Storage and Handling (16.4)].

PROGRAF injection must be diluted with 0.9% Sodium Chloride Injection or 5% Dextrose Injection to a concentration between 0.004 mg/mL and 0.02 mg/mL prior to use. Diluted infusion solution should be stored in glass or polyethylene containers and should be discarded after 24 hours. The diluted infusion solution should not be stored in a polyvinyl chloride (PVC) container due to decreased stability and the potential for extraction of phthalates. In situations where more dilute solutions are utilized (e.g., pediatric dosing, etc.), PVC-free tubing should likewise be used to minimize the potential for significant drug adsorption onto the tubing.

Parenteral drug products should be inspected visually for particulate matter and discoloration prior to administration, whenever solution and container permit.

Due to the chemical instability of tacrolimus in alkaline media, PROGRAF injection should not be mixed or co-infused with solutions of pH 9 or greater (e.g., ganciclovir or acyclovir).

2.8 Preparation and Administration Instructions of PROGRAF Granules

Tacrolimus can cause fetal harm. Follow applicable special handling and disposal procedures^1 [see How Supplied/ Storage and Handling (16.4)].

The required dose for PROGRAF Granules is calculated based on the weight of the patient. Use the minimum whole number of packets that corresponds to the required morning or evening dose. If the morning or evening dose is not covered by the whole number of packets, use one additional 0.2 mg packet to round up the dose. Do not use tubing, syringes and other equipment (cups) containing PVC to prepare or administer tacrolimus products. Do not sprinkle PROGRAF Granules on food. Prepare and administer PROGRAF Granules as follows:

• To prepare the dose, empty the entire contents of each PROGRAF Granules packet into a glass cup. Check for any remaining granules in the packet(s) and empty these into the cup.
• Add 1 to 2 tablespoons (15 to 30 milliliters) of room temperature drinking water to the cup containing the PROGRAF Granules.
• Mix and administer the entire contents of the cup. The granules will not completely dissolve. The suspension should be given immediately after preparation.
• For younger patients, the suspension can be drawn up via a non-PVC oral syringe that will be dispensed with the prescription.
• The cup or syringe should be rinsed with the same quantity of water (15 to 30 milliliters) and given to the patient to ensure all of the medication is taken.
• The pharmacy must dispense with the Instructions for Use. Alert the patient to read the Instructions for Use.

3 DOSAGE FORMS AND STRENGTHS

PROGRAF is available in the following dosage forms and strengths:

Capsules | Oblong, hard capsule for oral administration contains anhydrous tacrolimus USP as follows:; • 0.5 mg, light-yellow color, imprinted in red “0.5 mg” on the capsule cap and “607” on capsule body; • 1 mg, white color, imprinted in red “1 mg” on the capsule cap and “617” on capsule body; • 5 mg, grayish-red color, imprinted with white “5 mg” on the capsule cap and “657” on capsule body
Injection | 1 mL ampule for intravenous infusion contains anhydrous tacrolimus USP, 5 mg/mL
For Oral Suspension | Unit-dose packets with white granules for oral suspension contains anhydrous tacrolimus USP:; - 0.2 mg - 1 mg

4 CONTRAINDICATIONS

PROGRAF is contraindicated in patients with a hypersensitivity to tacrolimus. PROGRAF injection is contraindicated in patients with a hypersensitivity to HCO-60 (polyoxyl 60 hydrogenated castor oil). Hypersensitivity symptoms reported include dyspnea, rash, pruritus, and acute respiratory distress syndrome [see Adverse Reactions (6)].

5 WARNINGS AND PRECAUTIONS

5.1 Lymphoma and Other Malignancies

Patients receiving immunosuppressants, including PROGRAF, are at increased risk of developing lymphomas and other malignancies, particularly of the skin. The risk appears to be related to the intensity and duration of immunosuppression rather than to the use of any specific agent.

As usual for patients with increased risk for skin cancer, examine patients for skin changes; exposure to sunlight and UV light should be limited by wearing protective clothing and using a broad-spectrum sunscreen with a high protection factor.

Post-transplant lymphoproliferative disorder (PTLD) has been reported in immunosuppressed organ transplant recipients. The majority of PTLD events appear related to Epstein-Barr Virus (EBV) infection. The risk of PTLD appears greatest in those individuals who are EBV seronegative, a population which includes many young children. Monitor EBV serology during treatment.

5.2 Serious Infections

Patients receiving immunosuppressants, including PROGRAF, are at increased risk of developing bacterial, viral, fungal, and protozoal infections, including opportunistic infections. These infections may lead to serious, including fatal, outcomes. Serious viral infections reported include:

- Polyomavirus-associated nephropathy (PVAN), mostly due to BK virus infection
- JC virus-associated progressive multifocal leukoencephalopathy (PML)
- Cytomegalovirus infections: CMV seronegative transplant patients who receive an organ from a CMV seropositive donor disease are at higher risk of developing CMV viremia and CMV disease.

Monitor for the development of infection and adjust the immunosuppressive regimen to balance the risk of rejection with the risk of infection [see Adverse Reactions (6.1, 6.2)].

5.3 Not Interchangeable with Extended-Release Tacrolimus Products - Medication Errors

Medication errors, including substitution and dispensing errors, between tacrolimus immediate-release products and tacrolimus extended-release products were reported outside the U.S. This led to serious adverse reactions, including graft rejection, or other adverse reactions due to under- or overexposure to tacrolimus. PROGRAF is not interchangeable or substitutable for tacrolimus extended-release products. Changes between tacrolimus immediate-release and extended-release dosage forms must occur under physician supervision. Instruct patients and caregivers to recognize the appearance of PROGRAF dosage forms [see Dosage Forms and Strengths (3)] and to confirm with the healthcare provider if a different product is dispensed.

5.4 New Onset Diabetes After Transplant

PROGRAF was shown to cause new onset diabetes mellitus in clinical trials of kidney, liver, heart, or lung transplantation. New onset diabetes after transplantation may be reversible in some patients. African-American and Hispanic kidney transplant patients are at an increased risk. Blood glucose concentrations should be monitored closely in patients using PROGRAF [see Adverse Reactions (6.1)].

5.5 Nephrotoxicity due to PROGRAF and Drug Interactions

PROGRAF, like other calcineurin inhibitors, can cause acute or chronic nephrotoxicity in transplant patients due to its vasoconstrictive effect on renal vasculature, toxic tubulopathy and tubular-interstitial effects. Nephrotoxicity was reported in clinical trials [see Adverse Reactions (6.1)].

Acute renal impairment associated with tacrolimus toxicity can result in high serum creatinine, hyperkalemia, decreased secretion of urea and hyperuricemia, and is usually reversible. In patients with elevated serum creatinine and tacrolimus whole blood trough concentrations greater than the recommended range, consider dosage reduction or temporary interruption of tacrolimus administration.

The risk for nephrotoxicity may increase when PROGRAF is concomitantly administered with CYP3A inhibitors (by increasing tacrolimus whole blood concentrations) or drugs associated with nephrotoxicity (e.g., aminoglycosides, ganciclovir, amphotericin B, cisplatin, nucleotide reverse transcriptase inhibitors, protease inhibitors). When tacrolimus is used concurrently with other known nephrotoxic drugs, monitor renal function and tacrolimus blood concentrations, and adjust doses of both tacrolimus and/or concomitant medications during concurrent use [see Drug Interactions (7.2)].

5.6 Neurotoxicity

PROGRAF may cause a spectrum of neurotoxicities. The most severe neurotoxicities include posterior reversible encephalopathy syndrome (PRES), delirium, seizure and coma; others include tremors, paresthesias, headache, mental status changes, and changes in motor and sensory functions [see Adverse Reactions (6.1, 6.2)]. As symptoms may be associated with tacrolimus whole blood trough concentrations at or above the recommended range, monitor for neurologic symptoms and consider dosage reduction or discontinuation of PROGRAF if neurotoxicity occurs.

5.7 Hyperkalemia

Hyperkalemia has been reported with PROGRAF use. Serum potassium levels should be monitored. Careful consideration should be given prior to use of other agents also associated with hyperkalemia (e.g., potassium-sparing diuretics, ACE inhibitors, angiotensin receptor blockers) during PROGRAF therapy [see Adverse Reactions (6.1)]. Monitor serum potassium levels periodically during treatment.

5.8 Hypertension

Hypertension is a common adverse effect of PROGRAF therapy and may require antihypertensive therapy [see Adverse Reactions (6.1)]. The control of blood pressure can be accomplished with any of the common antihypertensive agents, though careful consideration should be given prior to use of antihypertensive agents associated with hyperkalemia (e.g., potassium-sparing diuretics, ACE inhibitors, angiotensin receptor blockers) [see Warnings and Precautions (5.7)]. Calcium-channel blocking agents may increase tacrolimus blood concentrations and therefore require dosage reduction of PROGRAF [see Drug Interactions (7.2)].

5.9 Anaphylactic Reactions with PROGRAF Injection

Anaphylactic reactions have occurred with injectables containing castor oil derivatives, including PROGRAF, in a small percentage of patients (0.6%). The exact cause of these reactions is not known. PROGRAF injection should be reserved for patients who are unable to take PROGRAF orally. Monitor patients for anaphylaxis when using the intravenous route of administration [see Dosage and Administration (2.1)].

5.10 Not Recommended for Use with Sirolimus

PROGRAF is not recommended for use with sirolimus:

• The use of sirolimus with PROGRAF in studies of de novo liver transplant patients was associated with an excess mortality, graft loss, and hepatic artery thrombosis (HAT), and is not recommended.

• The use of sirolimus (2 mg per day) with PROGRAF in heart transplant patients in a U.S. trial was associated with increased risk of renal function impairment, wound healing complications, and insulin-dependent post-transplant diabetes mellitus, and is not recommended [see Clinical Studies (14.3)].

• The use of sirolimus with PROGRAF may increase the risk of thrombotic microangiopathy [see Warnings and Precautions (5.16)].

5.11 Interactions with CYP3A4 Inhibitors and Inducers

When co-administering PROGRAF with strong CYP3A4 inhibitors (e.g., telaprevir, boceprevir, ritonavir, ketoconazole, itraconazole, voriconazole, clarithromycin) and strong inducers (e.g., rifampin, rifabutin), adjustments in the dosing regimen of PROGRAF and subsequent frequent monitoring of tacrolimus whole blood trough concentrations and tacrolimus-associated adverse reactions are recommended. A rapid, sharp rise in tacrolimus levels has been reported after co-administration with a strong CYP3A4 inhibitor, clarithromycin, despite an initial reduction of tacrolimus dose. Early and frequent monitoring of tacrolimus whole blood trough levels is recommended [see Drug Interactions (7.2)].

5.12 QT Prolongation

PROGRAF may prolong the QT/QTc interval and may cause Torsades de pointes. Avoid PROGRAF in patients with congenital long QT syndrome. In patients with congestive heart failure, bradyarrhythmias, those taking certain antiarrhythmic medications or other medicinal products that lead to QT prolongation, and those with electrolyte disturbances such as hypokalemia, hypocalcemia, or hypomagnesemia, consider obtaining electrocardiograms and monitoring electrolytes (magnesium, potassium, calcium) periodically during treatment.

When co-administering PROGRAF with other substrates and/or inhibitors of CYP3A4 that also have the potential to prolong the QT interval, a reduction in PROGRAF dose, frequent monitoring of tacrolimus whole blood concentrations, and monitoring for QT prolongation is recommended. Use of PROGRAF with amiodarone has been reported to result in increased tacrolimus whole blood concentrations with or without concurrent QT prolongation [see Drug Interactions (7.2)].

5.13 Myocardial Hypertrophy

Myocardial hypertrophy has been reported in infants, children, and adults, particularly those with high tacrolimus trough concentrations, and is generally manifested by echocardiographically demonstrated concentric increases in left ventricular posterior wall and interventricular septum thickness. This condition appears reversible in most cases following dose reduction or discontinuance of therapy. In patients who develop renal failure or clinical manifestations of ventricular dysfunction while receiving PROGRAF therapy, echocardiographic evaluation should be considered. If myocardial hypertrophy is diagnosed, dosage reduction or discontinuation of PROGRAF should be considered [see Adverse Reactions (6.2)].

5.14 Immunizations

Whenever possible, administer the complete complement of vaccines before transplantation and treatment with PROGRAF.

The use of live vaccines should be avoided during treatment with tacrolimus; examples include (not limited to) the following: intranasal influenza, measles, mumps, rubella, oral polio, BCG, yellow fever, varicella, and TY21a typhoid vaccines.

Inactivated vaccines noted to be safe for administration after transplantation may not be sufficiently immunogenic during treatment with PROGRAF.

5.15 Pure Red Cell Aplasia

Cases of pure red cell aplasia (PRCA) have been reported in patients treated with tacrolimus. A mechanism for tacrolimus-induced PRCA has not been elucidated. All patients reported risk factors for PRCA such as parvovirus B19 infection, underlying disease, or concomitant medications associated with PRCA. If PRCA is diagnosed, discontinuation of PROGRAF should be considered [see Adverse Reactions (6.2)].

5.16 Thrombotic Microangiopathy (Including Hemolytic Uremic Syndrome and Thrombotic Thrombocytopenic Purpura)

Cases of thrombotic microangiopathy (TMA), including hemolytic uremic syndrome (HUS) and thrombotic thrombocytopenic purpura (TTP), have been reported in patients treated with PROGRAF. TMA may have a multifactorial etiology. Risk factors for TMA that can occur in transplant patients include, for example, severe infections, graft-versus-host disease (GVHD), Human Leukocyte Antigen (HLA) mismatch, the use of calcineurin inhibitors and mammalian target of rapamycin (mTOR) inhibitors. These risk factors may, either alone or combined, contribute to the risk of TMA.

In patients with signs and symptoms of TMA, consider tacrolimus as a risk factor. Concurrent use of tacrolimus and mTOR inhibitors may contribute to the risk of TMA.

5.17 Cannabidiol Drug Interactions

When cannabidiol and PROGRAF are co-administered, closely monitor for an increase in tacrolimus blood levels and for adverse reactions suggestive of tacrolimus toxicity. A dose reduction of PROGRAF should be considered as needed when PROGRAF is co-administered with cannabidiol [see Dosage and Administration (2.2, 2.6) and Drug Interactions (7.3)].

6 ADVERSE REACTIONS

The following serious and otherwise important adverse drug reactions are discussed in greater detail in other sections of labeling:

- Lymphoma and Other Malignancies [see Warnings and Precautions (5.1)]
- Serious Infections [see Warnings and Precautions (5.2)]
- New Onset Diabetes After Transplant [see Warnings and Precautions (5.4)]
- Nephrotoxicity [see Warnings and Precautions (5.5)]
- Neurotoxicity [see Warnings and Precautions (5.6)]
- Hyperkalemia [see Warnings and Precautions (5.7)]
- Hypertension [see Warnings and Precautions (5.8)]
- Anaphylactic Reactions with PROGRAF Injection [see Warnings and Precautions (5.9)]
- Myocardial Hypertrophy [see Warnings and Precautions (5.13)]
- Pure Red Cell Aplasia [see Warnings and Precautions (5.15)]
- Thrombotic Microangiopathy, Including Hemolytic Uremic Syndrome and Thrombotic Thrombocytopenic Purpura [see Warnings and Precautions (5.16)]

6.1 Clinical Studies Experience

Because clinical trials are conducted under widely varying conditions, adverse reaction rates observed in the clinical trials of a drug cannot be directly compared to rates in the clinical trials of another drug and may not reflect the rates observed in practice. In addition, the clinical trials were not designed to establish comparative differences across study arms with regards to the adverse reactions discussed below.

Kidney Transplantation
The incidence of adverse reactions was determined in three randomized kidney transplant trials. One of the trials used azathioprine (AZA) and corticosteroids and two of the trials used mycophenolate mofetil (MMF) and corticosteroids concomitantly for maintenance immunosuppression.

PROGRAF-based immunosuppression in conjunction with azathioprine and corticosteroids following kidney transplantation was assessed in a trial where 205 patients received PROGRAF-based immunosuppression and 207 patients received cyclosporine-based immunosuppression. The trial population had a mean age of 43 years (mean ± SD was 43 ± 13 years on PROGRAF and 44 ± 12 years on cyclosporine arm), the distribution was 61% male, and the composition was White (58%), African-American (25%), Hispanic (12%), and Other (5%). The 12-month post-transplant information from this trial is presented below.

The most common adverse reactions (≥ 30%) observed in PROGRAF-treated kidney transplant patients are: infection, tremor, hypertension, abnormal renal function, constipation, diarrhea, headache, abdominal pain, insomnia, nausea, hypomagnesemia, urinary tract infection, hypophosphatemia, peripheral edema, asthenia, pain, hyperlipidemia, hyperkalemia, and anemia. Based on reported adverse reaction terms related to decreased renal function, nephrotoxicity was reported in approximately 52% of kidney transplantation patients.

Adverse reactions that occurred in ≥ 15% of kidney transplant patients treated with PROGRAF in conjunction with azathioprine are presented below:

Table 4. Kidney Transplantation: Adverse Reactions Occurring in ≥ 15% of Patients Treated with PROGRAF in Conjunction with Azathioprine (AZA)
 | PROGRAF/AZA (N = 205) | Cyclosporine/AZA (N = 207)
Nervous System
Tremor | 54% | 34%
Headache | 44% | 38%
Insomnia | 32% | 30%
Paresthesia | 23% | 16%
Dizziness | 19% | 16%
Gastrointestinal
Diarrhea | 44% | 41%
Nausea | 38% | 36%
Constipation | 35% | 43%
Vomiting | 29% | 23%
Dyspepsia | 28% | 20%
Cardiovascular
Hypertension | 50% | 52%
Chest Pain | 19% | 13%
Urogenital
Creatinine Increased | 45% | 42%
Urinary Tract Infection | 34% | 35%
Metabolic and Nutritional
Hypophosphatemia | 49% | 53%
Hypomagnesemia | 34% | 17%
Hyperlipemia | 31% | 38%
Hyperkalemia | 31% | 32%
Diabetes Mellitus | 24% | 9%
Hypokalemia | 22% | 25%
Hyperglycemia | 22% | 16%
Edema | 18% | 19%
Hemic and Lymphatic
Anemia | 30% | 24%
Leukopenia | 15% | 17%
Miscellaneous
Infection | 45% | 49%
Peripheral Edema | 36% | 48%
Asthenia | 34% | 30%
Abdominal Pain | 33% | 31%
Pain | 32% | 30%
Fever | 29% | 29%
Back Pain | 24% | 20%
Respiratory System
Dyspnea | 22% | 18%
Cough Increased | 18% | 15%
Musculoskeletal
Arthralgia | 25% | 24%
Skin
Rash | 17% | 12%
Pruritus | 15% | 7%

Two trials were conducted for PROGRAF-based immunosuppression in conjunction with MMF and corticosteroids. In the non-US trial (Study 1), the incidence of adverse reactions was based on 1195 kidney transplant patients that received PROGRAF (Group C, n = 403), or one of two cyclosporine (CsA) regimens (Group A, n = 384 and Group B, n = 408) in combination with MMF and corticosteroids; all patients, except those in one of the two cyclosporine groups, also received induction with daclizumab. The trial population had a mean age of 46 years (range 17 to 76); the distribution was 65% male, and the composition was 93% Caucasian. The 12-month post-transplant information from this trial is presented below.

Adverse reactions that occurred in ≥ 10% of kidney transplant patients treated with PROGRAF in conjunction with MMF in Study 1 [Note: This trial was conducted entirely outside of the United States. Such trials often report a lower incidence of adverse reactions in comparison to U.S. trials] are presented below:

Table 5. Kidney Transplantation: Adverse Reactions Occurring in ≥ 10% of Patients Treated with PROGRAF in Conjunction with MMF (Study 1)
 | PROGRAF (Group C); (N = 403) | Cyclosporine (Group A); (N = 384) | Cyclosporine (Group B); (N = 408)
Diarrhea | 25% | 16% | 13%
Urinary Tract Infection | 24% | 28% | 24%
Anemia | 17% | 19% | 17%
Hypertension | 13% | 14% | 12%
Leukopenia | 13% | 10% | 10%
Edema Peripheral | 11% | 12% | 13%
Hyperlipidemia | 10% | 15% | 13%
Key: Group A = CsA/MMF/CS, B = CsA/MMF/CS/Daclizumab, C = Tac/MMF/CS/Daclizumab
CsA = Cyclosporine, CS = Corticosteroids, Tac = Tacrolimus, MMF = mycophenolate mofetil

In the U.S. trial (Study 2) with PROGRAF-based immunosuppression in conjunction with MMF and corticosteroids, 424 kidney transplant patients received PROGRAF (n = 212) or cyclosporine (n = 212) in combination with MMF 1 gram twice daily, basiliximab induction, and corticosteroids. The trial population had a mean age of 48 years (range 17 to 77); the distribution was 63% male, and the composition was White (74%), African-American (20%), Asian (3%), and Other (3%). The 12-month post-transplant information from this trial is presented below.

Adverse reactions that occurred in ≥ 15% of kidney transplant patients treated with PROGRAF in conjunction with MMF in Study 2 are presented below:

Table 6. Kidney Transplantation: Adverse Reactions Occurring in ≥ 15% of Patients Treated with PROGRAF in Conjunction with MMF (Study 2)
 | PROGRAF/MMF | Cyclosporine/MMF
 | (N = 212) | (N = 212)
Gastrointestinal Disorders
Diarrhea | 44% | 26%
Nausea | 39% | 47%
Constipation | 36% | 41%
Vomiting | 26% | 25%
Dyspepsia | 18% | 15%
Injury, Poisoning, and Procedural Complications
Post-Procedural Pain | 29% | 27%
Incision Site Complication | 28% | 23%
Graft Dysfunction | 24% | 18%
Metabolism and Nutrition Disorders
Hypomagnesemia | 28% | 22%
Hypophosphatemia | 28% | 21%
Hyperkalemia | 26% | 19%
Hyperglycemia | 21% | 15%
Hyperlipidemia | 18% | 25%
Hypokalemia | 16% | 18%
Nervous System Disorders
Tremor | 34% | 20%
Headache | 24% | 25%
Blood and Lymphatic System Disorders
Anemia | 30% | 28%
Leukopenia | 16% | 12%
Miscellaneous
Edema Peripheral | 35% | 46%
Hypertension | 32% | 35%
Insomnia | 30% | 21%
Urinary Tract Infection | 26% | 22%
Blood Creatinine Increased | 23% | 23%

Less frequently observed adverse reactions in kidney transplantation patients are described under the subsection “Less Frequently Reported Adverse Reactions (> 3% and < 15%) in Liver, Kidney, and Heart Transplant Studies.”

Liver Transplantation

There were two randomized comparative liver transplant trials. In the U.S. trial, 263 adult and pediatric patients received tacrolimus and steroids and 266 patients received cyclosporine-based immunosuppressive regimen (CsA/AZA). The trial population had a mean age of 44 years (range 0.4 to 70); the distribution was 52% male, and the composition was White (78%), African-American (5%), Asian (2%), Hispanic (13%), and Other (2%). In the European trial, 270 patients received tacrolimus and steroids and 275 patients received CsA/AZA. The trial population had a mean age of 46 years (range 15 to 68); the distribution was 59% male, and the composition was White (95.4%), Black (1%), Asian (2%), and Other (2%).

The proportion of patients reporting more than one adverse event was > 99% in both the tacrolimus group and the CsA/AZA group. Precautions must be taken when comparing the incidence of adverse reactions in the U.S. trial to that in the European trial. The 12-month post-transplant information from the U.S. trial and from the European trial is presented below. The two trials also included different patient populations and patients were treated with immunosuppressive regimens of differing intensities. Adverse reactions reported in ≥ 15% in tacrolimus patients (combined trial results) are presented below for the two controlled trials in liver transplantation.

The most common adverse reactions (≥ 40%) observed in PROGRAF-treated liver transplant patients are: tremor, headache, diarrhea, hypertension, nausea, abnormal renal function, abdominal pain, insomnia, paresthesia, anemia, pain, fever, asthenia, hyperkalemia, hypomagnesemia, and hyperglycemia. These all occur with oral and IV administration of PROGRAF and some may respond to a reduction in dosing (e.g., tremor, headache, paresthesia, hypertension). Diarrhea was sometimes associated with other gastrointestinal complaints such as nausea and vomiting. Based on reported adverse reaction terms related to decreased renal function, nephrotoxicity was reported in approximately 40% and 36% of liver transplantation patients receiving PROGRAF in the U.S. and European randomized trials.

Table 7. Liver Transplantation: Adverse Reactions Occurring in ≥ 15% of Patients Treated with PROGRAF
 | U.S. TRIAL |  | EUROPEAN TRIAL
 | PROGRAF (N = 250) | Cyclosporine/ AZA (N = 250) | PROGRAF (N = 264) | Cyclosporine/ AZA (N = 265)
Nervous System
Headache | 64% | 60% | 37% | 26%
Insomnia | 64% | 68% | 32% | 23%
Tremor | 56% | 46% | 48% | 32%
Paresthesia | 40% | 30% | 17% | 17%
Gastrointestinal
Diarrhea | 72% | 47% | 37% | 27%
Nausea | 46% | 37% | 32% | 27%
LFT Abnormal | 36% | 30% | 6% | 5%
Anorexia | 34% | 24% | 7% | 5%
Vomiting | 27% | 15% | 14% | 11%
Constipation | 24% | 27% | 23% | 21%
Cardiovascular
Hypertension | 47% | 56% | 38% | 43%
Urogenital
Kidney Function Abnormal | 40% | 27% | 36% | 23%
Creatinine Increased | 39% | 25% | 24% | 19%
BUN Increased | 30% | 22% | 12% | 9%
Oliguria | 18% | 15% | 19% | 12%
Urinary Tract Infection | 16% | 18% | 21% | 19%
Metabolic and Nutritional
Hypomagnesemia | 48% | 45% | 16% | 9%
Hyperglycemia | 47% | 38% | 33% | 22%
Hyperkalemia | 45% | 26% | 13% | 9%
Hypokalemia | 29% | 34% | 13% | 16%
Hemic and Lymphatic
Anemia | 47% | 38% | 5% | 1%
Leukocytosis | 32% | 26% | 8% | 8%
Thrombocytopenia | 24% | 20% | 14% | 19%
Miscellaneous
Pain | 63% | 57% | 24% | 22%
Abdominal Pain | 59% | 54% | 29% | 22%
Asthenia | 52% | 48% | 11% | 7%
Fever | 48% | 56% | 19% | 22%
Back Pain | 30% | 29% | 17% | 17%
Ascites | 27% | 22% | 7% | 8%
Peripheral Edema | 26% | 26% | 12% | 14%
Respiratory System
Pleural Effusion | 30% | 32% | 36% | 35%
Dyspnea | 29% | 23% | 5% | 4%
Atelectasis | 28% | 30% | 5% | 4%
Skin and Appendages
Pruritus | 36% | 20% | 15% | 7%
Rash | 24% | 19% | 10% | 4%

Table 8. Pediatric Liver Transplantation: Adverse Reactions Occurring in > 10% of Patients Treated with PROGRAF Granules (STUDY 01-13)
 | PROGRAF Granules (N = 91) | Cyclosporine (N = 90)
Body as a Whole
Fever | 46% | 51%
Infection | 25% | 29%
Sepsis | 22% | 20%
CMV Infection | 15% | 24%
EBV Infection | 26% | 11%
Ascites | 17% | 20%
Peritonitis | 12% | 7%
Cardiovascular System
Hypertension | 39% | 47%
Digestive System
Liver Function Tests Abnormal | 37% | 28%
Diarrhea | 26% | 26%
Vomiting | 15% | 13%
Gastrointestinal Hemorrhage | 11% | 12%
Bile Duct Disorder | 12% | 8%
Gastroenteritis | 12% | 4%
Hemic and Lymphatic System
Anemia | 29% | 19%
Metabolic and Nutritional Disorders
Hypomagnesemia | 40% | 29%
Acidosis | 26% | 17%
Hyperkalemia | 12% | 10%
Respiratory System
Pleural Effusion | 22% | 19%
Bronchitis | 11% | 8%
Urogenital System
Kidney Function Abnormal | 13% | 14%

Less frequently observed adverse reactions in liver transplantation patients are described under the subsection “Less Frequently Reported Adverse Reactions (> 3% and < 15%) in Liver, Kidney, and Heart Transplant Studies.”

Heart Transplantation

The incidence of adverse reactions was determined based on two trials in primary orthotopic heart transplantation. In a trial conducted in Europe, 314 patients received a regimen of antibody induction, corticosteroids, and azathioprine (AZA) in combination with PROGRAF (n = 157) or cyclosporine (n = 157) for 18 months. The trial population had a mean age of 51 years (range 18 to 65); the distribution was 82% male, and the composition was White (96%), Black (3%), and Other (1%).

The most common adverse reactions (≥ 15%) observed in PROGRAF-treated heart transplant patients are: abnormal renal function, hypertension, diabetes mellitus, CMV infection, tremor, hyperglycemia, leukopenia, infection, anemia, bronchitis, pericardial effusion, urinary tract infection, and hyperlipemia. Based on reported adverse reaction terms related to decreased renal function, nephrotoxicity was reported in approximately 59% of heart transplantation patients in the European trial.

Adverse reactions in heart transplant patients in the European trial are presented below:

Table 9. Heart Transplantation: Adverse Reactions Occurring in ≥ 15% of Patients Treated with PROGRAF in Conjunction with Azathioprine (AZA)
 | PROGRAF/AZA (N = 157) | Cyclosporine/AZA (N = 157)
Cardiovascular System
Hypertension | 62% | 69%
Pericardial Effusion | 15% | 14%
Body as a Whole
CMV Infection | 32% | 30%
Infection | 24% | 21%
Metabolic and Nutritional Disorders
Diabetes Mellitus | 26% | 16%
Hyperglycemia | 23% | 17%
Hyperlipemia | 18% | 27%
Hemic and Lymphatic System
Anemia | 50% | 36%
Leukopenia | 48% | 39%
Urogenital System
Kidney Function Abnormal | 56% | 57%
Urinary Tract Infection | 16% | 12%
Respiratory System
Bronchitis | 17% | 18%
Nervous System
Tremor | 15% | 6%

In the European trial, the cyclosporine trough concentrations were above the pre-defined target range (i.e., 100 to 200 ng/mL) at Day 122 and beyond in 32% to 68% of the patients in the cyclosporine treatment arm, whereas the tacrolimus trough concentrations were within the pre-defined target range (i.e., 5 to 15 ng/mL) in 74% to 86% of the patients in the tacrolimus treatment arm.

In a U.S. trial, the incidence of adverse reactions was based on 331 heart transplant patients that received corticosteroids and PROGRAF in combination with sirolimus (n=109), PROGRAF in combination with MMF (n=107) or cyclosporine modified in combination with MMF (n=115) for 1 year. The trial population had a mean age of 53 years (range 18 to 75); the distribution was 78% male, and the composition was White (83%), African-American (13%) and Other (4%).
Only selected targeted treatment-emergent adverse reactions were collected in the U.S. heart transplantation trial. Those reactions that were reported at a rate of 15% or greater in patients treated with PROGRAF and MMF include the following: any target adverse reactions (99%), hypertension (89%), hyperglycemia requiring antihyperglycemic therapy (70%), hypertriglyceridemia (65%), anemia (hemoglobin < 10.0 g/dL) (65%), fasting blood glucose > 140 mg/dL (on two separate occasions) (61%), hypercholesterolemia (57%), hyperlipidemia (34%), WBCs < 3000 cells/mcL (34%), serious bacterial infections (30%), magnesium < 1.2 mEq/L (24%), platelet count < 75,000 cells/mcL (19%), and other opportunistic infections (15%).

Other targeted treatment-emergent adverse reactions in PROGRAF-treated patients occurred at a rate of less than 15%, and include the following: Cushingoid features, impaired wound healing, hyperkalemia, Candida infection, and CMV infection/syndrome. Other less frequently observed adverse reactions in heart transplantation patients are described under the subsection “Less Frequently Reported Adverse Reactions (> 3% and < 15%) in Liver, Kidney and Heart Transplant Studies.”

New Onset Diabetes After Transplant

Kidney Transplantation

New Onset Diabetes After Transplant (NODAT) is defined as a composite of fasting plasma glucose ≥ 126 mg/dL, HbA1C ≥ 6%, insulin use ≥ 30 days, or oral hypoglycemic use. In a trial in kidney transplant patients (Study 2), NODAT was observed in 75% in the PROGRAF-treated and 61% in the NEORAL-treated patients without pre-transplant history of diabetes mellitus (Table 10) [see Clinical Studies (14.1)].

Table 10. Incidence of New Onset Diabetes After Transplant at 1 year in Kidney Transplant Recipients in a Phase 3 Trial (Study 2)
Parameter | Treatment Group
Parameter | PROGRAF/MMF (N = 212) | NEORAL/MMF (N = 212)
NODAT | 112/150 (75%) | 93/152 (61%)
Fasting Plasma Glucose ≥ 126 mg/dL | 96/150 (64%) | 80/152 (53%)
HbA1C ≥ 6% | 59/150 (39%) | 28/152 (18%)
Insulin Use ≥ 30 days | 9/150 (6%) | 4/152 (3%)
Oral Hypoglycemic Use | 15/150 (10%) | 5/152 (3%)

In early trials of PROGRAF, Post-Transplant Diabetes Mellitus (PTDM) was evaluated with a more limited criterion of “use of insulin for 30 or more consecutive days with < 5-day gap” in patients without a prior history of insulin-dependent diabetes mellitus or non-insulin dependent diabetes mellitus. Data are presented in Tables 11 to 14. PTDM was reported in 20% of PROGRAF/Azathioprine (AZA)-treated kidney transplant patients without pre-transplant history of diabetes mellitus in a Phase 3 trial (Table 11). The median time to onset of PTDM was 68 days. Insulin dependence was reversible in 15% of these PTDM patients at one year and in 50% at 2 years post-transplant. African-American and Hispanic kidney transplant patients were at an increased risk of development of PTDM (Table 12).

Table 11. Incidence of Post-Transplant Diabetes Mellitus and Insulin Use at 2 Years in Kidney Transplant Recipients in a Phase 3 Trial using Azathioprine (AZA)
Status of PTDM [Use of insulin for 30 or more consecutive days, with < 5-day gap, without a prior history of insulin-dependent diabetes mellitus or non-insulin dependent diabetes mellitus.] | PROGRAF/AZA | CsA/AZA
Patients without pre-transplant history of diabetes mellitus | 151 | 151
New onset PTDM, 1st Year | 30/151 (20%) | 6/151 (4%)
Still insulin-dependent at one year in those without prior history of diabetes | 25/151 (17%) | 5/151 (3%)
New onset PTDM post 1 year | 1 | 0
Patients with PTDM at 2 years | 16/151 (11%) | 5/151 (3%)

Table 12. Development of Post-Transplant Diabetes Mellitus by Race or Ethnicity and by Treatment Group During First Year Post Kidney Transplantation in a Phase 3 Trial
Patient Race | Patients Who Developed PTDM [Use of insulin for 30 or more consecutive days, with < 5-day gap, without a prior history of insulin-dependent diabetes mellitus or non-insulin dependent diabetes mellitus.]
Patient Race | PROGRAF | Cyclosporine
African-American | 15/41 (37%) | 3 (8%)
Hispanic | 5/17 (29%) | 1 (6%)
Caucasian | 10/82 (12%) | 1 (1%)
Other | 0/11 (0%) | 1 (10%)
Total | 30/151 (20%) | 6 (4%)

Liver Transplantation

Insulin-dependent PTDM was reported in 18% and 11% of PROGRAF-treated liver transplant patients and was reversible in 45% and 31% of these patients at 1 year post-transplant, in the U.S. and European randomized trials, respectively (Table 13). Hyperglycemia was associated with the use of PROGRAF in 47% and 33% of liver transplant recipients in the U.S. and European randomized trials, respectively, and may require treatment [see Adverse Reactions (6.1)].

Table 13. Incidence of Post-Transplant Diabetes Mellitus and Insulin Use at 1 Year in Liver Transplant Recipients
Status of PTDM [Use of insulin for 30 or more consecutive days, with < 5-day gap, without a prior history of insulin-dependent diabetes mellitus or non-insulin dependent diabetes mellitus.] | US Trial |  | European Trial
Status of PTDM [Use of insulin for 30 or more consecutive days, with < 5-day gap, without a prior history of insulin-dependent diabetes mellitus or non-insulin dependent diabetes mellitus.] | PROGRAF | Cyclosporine | PROGRAF | Cyclosporine
Patients at risk [Patients without pre-transplant history of diabetes mellitus.] | 239 | 236 | 239 | 249
New Onset PTDM | 42 (18%) | 30 (13%) | 26 (11%) | 12 (5%)
Patients still on insulin at 1 year | 23 (10%) | 19 (8%) | 18 (8%) | 6 (2%)

Heart Transplantation

Insulin-dependent PTDM was reported in 13% and 22% of PROGRAF-treated heart transplant patients receiving mycophenolate mofetil (MMF) or azathioprine (AZA) and was reversible in 30% and 17% of these patients at one year post-transplant, in the U.S. and European randomized trials, respectively (Table 14). Hyperglycemia, defined as two fasting plasma glucose levels ≥ 126 mg/dL, was reported with the use of PROGRAF plus MMF or AZA in 32% and 35% of heart transplant recipients in the U.S. and European randomized trials, respectively, and may require treatment [see Adverse Reactions (6.1)].

Table 14. Incidence of Post-Transplant Diabetes Mellitus and Insulin Use at 1 Year in Heart Transplant Recipients
Status of PTDM [Use of insulin for 30 or more consecutive days without a prior history of insulin-dependent diabetes mellitus or non-insulin dependent diabetes mellitus.] | US Trial |  | European Trial
Status of PTDM [Use of insulin for 30 or more consecutive days without a prior history of insulin-dependent diabetes mellitus or non-insulin dependent diabetes mellitus.] | PROGRAF/MMF | Cyclosporine/MMF | PROGRAF/AZA | Cyclosporine/AZA
Patients at risk [Patients without pre-transplant history of diabetes mellitus.] | 75 | 83 | 132 | 138
New Onset PTDM | 10 (13%) | 6 (7%) | 29 (22%) | 5 (4%)
Patients still on insulin at 1 year [7-12 months for the U.S. trial.] | 7 (9%) | 1 (1%) | 24 (18%) | 4 (3%)

Less Frequently Reported Adverse Reactions (> 3% and < 15%) in Liver, Kidney, and Heart Transplant Studies

The following adverse reactions were reported in either liver, kidney, and/or heart transplant recipients who were treated with tacrolimus in clinical trials.

- Nervous System: Abnormal dreams, agitation, amnesia, anxiety, confusion, convulsion, crying, depression, elevated mood, emotional lability, encephalopathy, hemorrhagic stroke, hallucinations, hypertonia, incoordination, monoparesis, myoclonus, nerve compression, nervousness, neuralgia, neuropathy, paralysis flaccid, psychomotor skills impaired, psychosis, quadriparesis, somnolence, thinking abnormal, vertigo, writing impaired
- Special Senses: Abnormal vision, amblyopia, ear pain, otitis media, tinnitus
- Gastrointestinal: Cholangitis, cholestatic jaundice, duodenitis, dysphagia, esophagitis, flatulence, gastritis, gastroesophagitis, gastrointestinal hemorrhage, GGT increase, GI disorder, GI perforation, hepatitis, hepatitis granulomatous, ileus, increased appetite, jaundice, liver damage, esophagitis ulcerative, oral moniliasis, pancreatic pseudocyst, stomatitis
- Cardiovascular: Abnormal ECG, angina pectoris, arrhythmia, atrial fibrillation, atrial flutter, bradycardia, cardiac fibrillation, cardiopulmonary failure, congestive heart failure, deep thrombophlebitis, echocardiogram abnormal, electrocardiogram QRS complex abnormal, electrocardiogram ST segment abnormal, heart failure, heart rate decreased, hemorrhage, hypotension, phlebitis, postural hypotension, syncope, tachycardia, thrombosis, vasodilatation
- Urogenital: Acute kidney failure, albuminuria, BK nephropathy, bladder spasm, cystitis, dysuria, hematuria, hydronephrosis, kidney failure, kidney tubular necrosis, nocturia, pyuria, toxic nephropathy, urge incontinence, urinary frequency, urinary incontinence, urinary retention, vaginitis
- Metabolic/Nutritional: Acidosis, alkaline phosphatase increased, alkalosis, ALT (SGPT) increased, AST (SGOT) increased, bicarbonate decreased, bilirubinemia, dehydration, GGT increased, gout, healing abnormal, hypercalcemia, hypercholesterolemia, hyperphosphatemia, hyperuricemia, hypervolemia, hypocalcemia, hypoglycemia, hyponatremia, hypoproteinemia, lactic dehydrogenase increased, weight gain
- Endocrine: Cushing’s syndrome
- Hemic/Lymphatic: Coagulation disorder, ecchymosis, hematocrit increased, hypochromic anemia, leukocytosis, polycythemia, prothrombin decreased, serum iron decreased
- Miscellaneous: Abdomen enlarged, abscess, accidental injury, allergic reaction, cellulitis, chills, fall, flu syndrome, generalized edema, hernia, mobility decreased, peritonitis, photosensitivity reaction, sepsis, temperature intolerance, ulcer
- Musculoskeletal: Arthralgia, cramps, generalized spasm, leg cramps, myalgia, myasthenia, osteoporosis
- Respiratory: Asthma, emphysema, hiccups, lung function decreased, pharyngitis, pneumonia, pneumothorax, pulmonary edema, rhinitis, sinusitis, voice alteration
- Skin: Acne, alopecia, exfoliative dermatitis, fungal dermatitis, herpes simplex, herpes zoster, hirsutism, neoplasm skin benign, skin discoloration, skin ulcer, sweating

Lung Transplantation

Adverse reactions in lung transplant patients were similar to those in kidney, liver, or heart transplant patients treated with PROGRAF [see Adverse Reactions (6.2)].

6.2 Postmarketing Experience

The following adverse reactions have been reported from worldwide marketing experience with tacrolimus. Because these reactions are reported voluntarily from a population of uncertain size, it is not always possible to reliably estimate their frequency or establish a causal relationship to drug exposure. Decisions to include these reactions in labeling are typically based on one or more of the following factors: (1) seriousness of the reaction, (2) frequency of the reporting, or (3) strength of causal connection to the drug.

Other reactions include:

- Cardiovascular: Atrial fibrillation, atrial flutter, cardiac arrhythmia, cardiac arrest, electrocardiogram T wave abnormal, flushing, myocardial infarction, myocardial ischemia, pericardial effusion, QT prolongation, Torsades de pointes, venous thrombosis deep limb, ventricular extrasystoles, ventricular fibrillation, myocardial hypertrophy
- Gastrointestinal: Bile duct stenosis, colitis, enterocolitis, gastroenteritis, gastroesophageal reflux disease, hepatic cytolysis, hepatic necrosis, hepatotoxicity, impaired gastric emptying, liver fatty, mouth ulceration, pancreatitis hemorrhagic, pancreatitis necrotizing, stomach ulcer, veno-occlusive liver disease
- Hemic/Lymphatic: Agranulocytosis, disseminated intravascular coagulation, hemolytic anemia, neutropenia, febrile neutropenia, pancytopenia, thrombocytopenic purpura, thrombotic thrombocytopenic purpura, pure red cell aplasia, thrombotic microangiopathy
- Infections: Cases of progressive multifocal leukoencephalopathy (PML), sometimes fatal; polyoma virus-associated nephropathy (PVAN) including graft loss
- Metabolic/Nutritional: Glycosuria, increased amylase including pancreatitis, weight decreased
- Miscellaneous: Feeling hot and cold, feeling jittery, hot flushes, multi-organ failure, primary graft dysfunction
- Musculoskeletal and Connective Tissue Disorders: Pain in extremity including Calcineurin-Inhibitor Induced Pain Syndrome (CIPS)
- Nervous System: Carpal tunnel syndrome, cerebral infarction, hemiparesis, leukoencephalopathy, mental disorder, mutism, posterior reversible encephalopathy syndrome (PRES), progressive multifocal leukoencephalopathy (PML), quadriplegia, speech disorder, syncope
- Respiratory: Acute respiratory distress syndrome, interstitial lung disease, lung infiltration, respiratory distress, respiratory failure
- Skin: Stevens-Johnson syndrome, toxic epidermal necrolysis
- Special Senses: Blindness, optic neuropathy, blindness cortical, hearing loss including deafness, photophobia
- Urogenital: Acute renal failure, cystitis hemorrhagic, hemolytic-uremic syndrome

Postmarketing Adverse Reactions in Lung Transplantation

Based on U.S. Scientific Registry of Transplant Recipients (SRTR) data, published clinical trials, and postmarketing reports, the safety profile for lung transplant patients treated with PROGRAF is consistent with the safety profile in kidney, liver, and heart transplant patients treated with PROGRAF. The primary adverse reactions described include renal dysfunction, infection, diabetes, gastrointestinal disturbances (e.g., diarrhea), hypertension, and neurological events (e.g., tremor). As expected, lung transplant patients have a higher incidence of pulmonary complications (e.g., pneumonia, bronchiolitis obliterans syndrome) than other solid organ transplant patients, which is in part due to the underlying disease and to the nature of the transplanted organ.

7 DRUG INTERACTIONS

7.1 Mycophenolic Acid

When PROGRAF is prescribed with a given dose of a mycophenolic acid (MPA) product, exposure to MPA is higher with PROGRAF co-administration than with cyclosporine co-administration with MPA, because cyclosporine interrupts the enterohepatic recirculation of MPA while tacrolimus does not. Monitor for MPA-associated adverse reactions and reduce the dose of concomitantly administered mycophenolic acid products as needed.

7.2 Effects of Other Drugs on PROGRAF

Table 15 displays the effects of other drugs on PROGRAF.

Table 15. Effects of Other Drugs/Substances on PROGRAF [PROGRAF dosage adjustment recommendation based on observed effect of co-administered drug on tacrolimus exposures [see Clinical Pharmacology (12.3)], literature reports of altered tacrolimus exposures, or the other drug’s known CYP3A inhibitor/inducer status.]
Drug/Substance Class or Name | Drug Interaction Effect | Recommendations
Grapefruit or grapefruit juice [High dose or double strength grapefruit juice is a strong CYP3A inhibitor; low dose or single strength grapefruit juice is a moderate CYP3A inhibitor.] | May increase tacrolimus whole blood trough concentrations and increase the risk of serious adverse reactions (e.g., neurotoxicity, QT prolongation) [see Warnings and Precautions (5.6, 5.11, 5.12)]. | Avoid grapefruit or grapefruit juice.
Strong CYP3A Inducers [Strong CYP3A inhibitor/inducer, based on reported effect on exposures to tacrolimus along with supporting in vitro CYP3A inhibitor/inducer data, or based on drug-drug interaction studies with midazolam (sensitive CYP3A probe substrate).] :; Antimycobacterials (e.g., rifampin, rifabutin), anticonvulsants (e.g., phenytoin, carbamazepine and phenobarbital), St John’s wort | May decrease tacrolimus whole blood trough concentrations and increase the risk of rejection [see Warnings and Precautions (5.11)]. | Increase PROGRAF dose and monitor tacrolimus whole blood trough concentrations [see Dosage and Administration (2.2, 2.6) and Clinical Pharmacology (12.3)].
Strong CYP3A Inhibitors:; Protease inhibitors (e.g., nelfinavir, telaprevir, boceprevir, ritonavir), azole antifungals (e.g., voriconazole, posaconazole, itraconazole, ketoconazole), antibiotics (e.g., clarithromycin, troleandomycin, chloramphenicol), nefazodone, letermovir, Schisandra sphenanthera extracts | May increase tacrolimus whole blood trough concentrations and increase the risk of serious adverse reactions (e.g., neurotoxicity, QT prolongation). A rapid, sharp rise in tacrolimus levels may occur early, despite an immediate reduction of tacrolimus dose [see Warnings and Precautions (5.6, 5.11, 5.12)]. | Reduce PROGRAF dose (for voriconazole and posaconazole, give one-third of the original dose) and adjust dose based on tacrolimus whole blood trough concentrations [see Dosage and Administration (2.2, 2.6) and Clinical Pharmacology (12.3)]. Early and frequent monitoring of tacrolimus whole blood trough levels should start within 1-3 days and continue monitoring as necessary [see Warnings and Precautions (5.11)].
Mild or Moderate CYP3A Inhibitors:; Clotrimazole, antibiotics (e.g., erythromycin, fluconazole), calcium channel blockers (e.g., verapamil, diltiazem, nifedipine, nicardipine), amiodarone, danazol, ethinyl estradiol, cimetidine, lansoprazole and omeprazole | May increase tacrolimus whole blood trough concentrations and increase the risk of serious adverse reactions (e.g., neurotoxicity, QT prolongation) [see Warnings and Precautions (5.6, 5.11, 5.12)]. | Monitor tacrolimus whole blood trough concentrations and reduce PROGRAF dose if needed [see Dosage and Administration (2.2, 2.6) and Clinical Pharmacology (12.3)].
Other drugs, such as:; Magnesium and aluminum hydroxide antacids Metoclopramide | May increase tacrolimus whole blood trough concentrations and increase the risk of serious adverse reactions (e.g., neurotoxicity, QT prolongation) [see Warnings and Precautions (5.6, 5.11, 5.12)]. | Monitor tacrolimus whole blood trough concentrations and reduce PROGRAF dose if needed [see Dosage and Administration (2.2, 2.6) and Clinical Pharmacology (12.3)].
Mild or Moderate CYP3A Inducers; Methylprednisolone, prednisone | May decrease tacrolimus whole blood trough concentrations. | Monitor tacrolimus whole blood trough concentrations and adjust PROGRAF dose if needed [see Dosage and Administration (2.2, 2.6)].
Caspofungin | May decrease tacrolimus whole blood trough concentrations. | Monitor tacrolimus whole blood trough concentrations and adjust PROGRAF dose if needed [see Dosage and Administration (2.2, 2.6)].

Direct Acting Antiviral (DAA) Therapy

The pharmacokinetics of tacrolimus may be impacted by changes in liver function during DAA therapy, related to clearance of HCV virus. Close monitoring and potential dose adjustment of PROGRAF is warranted to ensure continued efficacy and safety [see Dosage and Administration (2.2, 2.6)].

7.3 Cannabidiol

The blood levels of tacrolimus may increase upon concomitant use with cannabidiol. When cannabidiol and PROGRAF are co-administered, closely monitor for an increase in tacrolimus blood levels and for adverse reactions suggestive of tacrolimus toxicity. A dose reduction of PROGRAF should be considered as needed when PROGRAF is co-administered with cannabidiol [see Dosage and Administration (2.2, 2.6) and Warnings and Precautions (5.17)].

8 USE IN SPECIFIC POPULATIONS

8.1 Pregnancy

Pregnancy Exposure Registry

There is a pregnancy registry that monitors pregnancy outcomes in women exposed to PROGRAF during pregnancy.

The Transplantation Pregnancy Registry International (TPRI) is a voluntary pregnancy exposure registry that monitors outcomes of pregnancy in female transplant recipients and those fathered by male transplant recipients exposed to immunosuppressants including tacrolimus. Healthcare providers are encouraged to advise their patients to register by contacting the Transplantation Pregnancy Registry International at 1-877-955-6877 or https://www.transplantpregnancyregistry.org/.

Risk Summary

Tacrolimus can cause fetal harm when administered to a pregnant woman. Data from postmarketing surveillance and TPRI suggest that infants exposed to tacrolimus in utero are at a risk of prematurity, birth defects/congenital anomalies, low birth weight, and fetal distress [see Human Data]. Advise pregnant women of the potential risk to the fetus.

Administration of oral tacrolimus to pregnant rabbits and rats throughout the period of organogenesis was associated with maternal toxicity/lethality, and an increased incidence of abortion, malformation and embryofetal death at clinically relevant doses (0.5 to 6.9 times the recommended clinical dose range [0.2 to 0.075 mg/kg/day], on a mg/m^2 basis).

Administration of oral tacrolimus to pregnant rats after organogenesis and throughout lactation produced maternal toxicity, effects on parturition, reduced pup viability and reduced pup weight at clinically relevant doses (0.8 to 6.9 times the recommended clinical dose range, on a mg/m^2 basis). Administration of oral tacrolimus to rats prior to mating, and throughout gestation and lactation produced maternal toxicity/lethality, marked effects on parturition, embryofetal loss, malformations, and reduced pup viability at clinically relevant doses (0.8 to 6.9 times the recommended clinical dose range, on a mg/m^2 basis). Interventricular septal defects, hydronephrosis, craniofacial malformations and skeletal effects were observed in offspring that died [see Animal Data].

The background risk of major birth defects and miscarriage in the indicated population is unknown. In the U.S. general population, the estimated background risk of major birth defects and miscarriage in clinically recognized pregnancies is 2 to 4% and 15 to 20%, respectively.

Clinical Considerations

Disease-Associated Maternal and/or Embryo-Fetal Risk

Risks during pregnancy are increased in organ transplant recipients.

The risk of premature delivery following transplantation is increased. Pre-existing hypertension and diabetes confer additional risk to the pregnancy of an organ transplant recipient. Pre-gestational and gestational diabetes are associated with birth defects/congenital anomalies, hypertension, low birth weight and fetal death.

Cholestasis of pregnancy (COP) was reported in 7% of liver or liver-kidney (LK) transplant recipients, compared with approximately 1% of pregnancies in the general population. However, COP symptoms resolved postpartum and no long-term effects on the offspring were reported.

Maternal Adverse Reactions

PROGRAF may increase hyperglycemia in pregnant women with diabetes (including gestational diabetes). Monitor maternal blood glucose levels regularly [see Warnings and Precautions (5.4)].

PROGRAF may exacerbate hypertension in pregnant women and increase pre-eclampsia. Monitor and control blood pressure [see Warnings and Precautions (5.7, 5.8)].

Fetal/Neonatal Adverse Reactions

Renal dysfunction, transient neonatal hyperkalemia and low birth weight have been reported at the time of delivery in infants of mothers taking PROGRAF.

Labor or Delivery

There is an increased risk for premature delivery (< 37 weeks) following transplantation and maternal exposure to PROGRAF.

Data

Human Data

There are no adequate and well controlled studies on the effects of tacrolimus in human pregnancy. Safety data from the TPRI and postmarketing surveillance suggest infants exposed to tacrolimus in utero have an increased risk for miscarriage, pre-term delivery (< 37 weeks), low birth weight (< 2500 g), birth defects/congenital anomalies and fetal distress.

TPRI reported 450 and 241 total pregnancies in kidney and liver transplant recipients exposed to tacrolimus, respectively. The TPRI pregnancy outcomes are summarized in Table 16. In the table below, the number of recipients exposed to tacrolimus concomitantly with mycophenolic acid (MPA) products during the preconception and first trimester periods is high (27% and 29% for renal and liver transplant recipients, respectively). Because MPA products may also cause birth defects, the birth defect rate may be confounded and this should be taken into consideration when reviewing the data, particularly for birth defects. Birth defects observed include cardiac malformations, craniofacial malformations, renal/urogenital disorders, skeletal abnormalities, neurological abnormalities and multiple malformations.

Table 16. TPRI Reported Pregnancy Outcomes in Transplant Recipients with Exposure to Tacrolimus
 | Kidney | Liver
Pregnancy Outcomes [Includes multiple births and terminations.] | 462 | 253
Miscarriage | 24.5% | 25%
Live births | 331 | 180
Pre-term delivery (< 37 weeks) | 49% | 42%
Low birth weight (< 2500 g) | 42% | 30%
Birth defects | 8% [Birth defect rate confounded by concomitant MPA products exposure in over half of offspring with birth defects.] | 5%

Additional information reported by TPRI in pregnant transplant patients receiving tacrolimus included diabetes during pregnancy in 9% of kidney recipients and 13% of liver recipients, and hypertension during pregnancy in 53% of kidney recipients and 16.2% of liver recipients.

Animal Data

Administration of oral tacrolimus to pregnant rabbits throughout organogenesis produced maternal toxicity and abortion at 0.32 mg/kg (0.5 to 1.4 times the recommended clinical dose range [0.2 to 0.075 mg/kg/day], on a mg/m^2 basis). At 1 mg/kg (1.6 to 4.3 times the recommended clinical dose range), embryofetal lethality and fetal malformations (ventricular hypoplasia, interventricular septal defect, bulbous aortic arch, stenosis of ductus arteriosus, omphalocele, gallbladder agenesis, skeletal anomalies) were observed. Administration of 3.2 mg/kg oral tacrolimus (2.6 to 6.9 times the recommended clinical dose range) to pregnant rats throughout organogenesis produced maternal toxicity/lethality, embryofetal lethality and decreased fetal body weight in the offspring of C-sectioned dams; and decreased pup viability and interventricular septal defect in offspring of dams that delivered.

In a peri-/postnatal development study, oral administration of tacrolimus to pregnant rats during late gestation (after organogenesis) and throughout lactation produced maternal toxicity, effects on parturition, and reduced pup viability at 3.2 mg/kg (2.6 to 6.9 times the recommended clinical dose range); among these pups that died early, an increased incidence of kidney hydronephrosis was observed. Reduced pup weight was observed at 1.0 mg/kg (0.8 to 2.2 times the recommended clinical dose range).

Administration of oral tacrolimus to rats prior to mating, and throughout gestation and lactation, produced maternal toxicity/lethality, embryofetal loss and reduced pup viability at 3.2 mg/kg (2.6 to 6.9 times the recommended clinical dose range). Interventricular septal defects, hydronephrosis, craniofacial malformations and skeletal effects were observed in offspring that died. Effects on parturition (incomplete delivery of nonviable pups) were observed at 1 mg/kg (0.8 to 2.2 times the recommended clinical dose range) [see Nonclinical Toxicology (13.1)].

8.2 Lactation

Risk Summary

Controlled lactation studies have not been conducted in humans; however, tacrolimus has been reported to be present in human milk. The effects of tacrolimus on the breastfed infant, or on milk production have not been assessed. Tacrolimus is excreted in rat milk and in peri-/postnatal rat studies; exposure to tacrolimus during the postnatal period was associated with developmental toxicity in the offspring at clinically relevant doses [see Use in Specific Populations (8.1) and Nonclinical Toxicology (13.1)].

The developmental and health benefits of breastfeeding should be considered along with the mother’s clinical need for PROGRAF and any potential adverse effects on the breastfed child from PROGRAF or from the underlying maternal condition.

8.3 Females and Males of Reproductive Potential

Contraception

PROGRAF can cause fetal harm when administered to pregnant women. Advise female and male patients of reproductive potential to speak to their healthcare provider on family planning options including appropriate contraception prior to starting treatment with PROGRAF [see Use in Specific Populations (8.1) and Nonclinical Toxicology (13.1)].

Infertility

Based on findings in animals, male and female fertility may be compromised by treatment with PROGRAF [see Nonclinical Toxicology (13.1)].

8.4 Pediatric Use

Safety and effectiveness have been established in pediatric liver, kidney, heart, and lung transplant patients.

Liver Transplantation

Safety and efficacy using PROGRAF Granules in pediatric de novo liver transplant patients less than 16 years of age are based on evidence from active controlled studies that included 56 pediatric patients, 31 of which received PROGRAF, and supported by two pharmacokinetic and safety studies in 151 children who received PROGRAF. Additionally, 122 pediatric patients were studied in an uncontrolled trial of tacrolimus in living related donor liver transplantation. Dose adjustments were made in the PK studies based on clinical status and whole blood concentrations. Pediatric patients generally required higher doses of PROGRAF to maintain blood trough concentrations of tacrolimus similar to adult patients [see Dosage and Administration (2.3), Adverse Reactions (6.1), Clinical Pharmacology (12.3) and Clinical Studies (14.2)].

Kidney and Heart Transplantation

Use of PROGRAF capsules and PROGRAF Granules in pediatric kidney and heart transplant patients is supported by adequate and well-controlled studies and pharmacokinetic data in adult kidney and heart transplant patients with additional pharmacokinetic data in pediatric kidney and heart transplant patients and safety data in pediatric liver transplant patients [see Dosage and Administration (2.3) and Clinical Pharmacology (12.3)].

Lung Transplantation

The use of PROGRAF capsules and PROGRAF Granules in pediatric lung transplantation is supported by the experience in the U.S. Scientific Registry of Transplant Recipients (SRTR) including 450 pediatric patients receiving tacrolimus immediate-release products in combination with mycophenolate mofetil and 72 pediatric patients receiving tacrolimus immediate-release products in combination with azathioprine between 1999-2017.

8.5 Geriatric Use

Clinical trials of PROGRAF did not include sufficient numbers of subjects aged 65 and over to determine whether they respond differently from younger subjects. Other reported clinical experience has not identified differences in responses between the elderly and younger patients. In general, dose selection for an elderly patient should be cautious, usually starting at the low end of the dosing range, reflecting the greater frequency of decreased hepatic, renal, or cardiac function, and of concomitant disease or other drug therapy.

8.6 Renal Impairment

The pharmacokinetics of PROGRAF in patients with renal impairment was similar to that in healthy volunteers with normal renal function. However, consideration should be given to dosing PROGRAF at the lower end of the therapeutic dosing range in patients who have received a liver or heart transplant and have pre-existing renal impairment. Further reductions in dose below the targeted range may be required [see Dosage and Administration (2.4) and Clinical Pharmacology (12.3)].

8.7 Hepatic Impairment

The mean clearance of tacrolimus was substantially lower in patients with severe hepatic impairment (mean Child-Pugh score: > 10) compared to healthy volunteers with normal hepatic function. Close monitoring of tacrolimus trough concentrations is warranted in patients with hepatic impairment [see Clinical Pharmacology (12.3)].

The use of PROGRAF in liver transplant recipients experiencing post-transplant hepatic impairment may be associated with increased risk of developing renal insufficiency related to high whole blood trough concentrations of tacrolimus. These patients should be monitored closely and dosage adjustments should be considered. Some evidence suggests that lower doses should be used in these patients [see Dosage and Administration (2.5) and Clinical Pharmacology (12.3)].

8.8 Race or Ethnicity

African-American patients may need to be titrated to higher dosages to attain comparable trough concentrations compared to Caucasian patients [see Dosage and Administration (2.2) and Clinical Pharmacology (12.3)].

African-American and Hispanic patients are at increased risk for new onset diabetes after transplant. Monitor blood glucose concentrations and treat appropriately [see Warnings and Precautions (5.4)].

10 OVERDOSAGE

Limited overdosage experience is available. Acute overdosages of up to 30 times the intended dose have been reported. Almost all cases have been asymptomatic and all patients recovered with no sequelae. Acute overdosage was sometimes followed by adverse reactions consistent with those reported with the use of PROGRAF [see Adverse Reactions (6.1, 6.2)], including tremors, abnormal renal function, hypertension, and peripheral edema; in one case of acute overdosage, transient urticaria and lethargy were observed. Based on the poor aqueous solubility and extensive erythrocyte and plasma protein binding, it is anticipated that tacrolimus is not dialyzable to any significant extent; there is no experience with charcoal hemoperfusion. The oral use of activated charcoal has been reported in treating acute overdoses, but experience has not been sufficient to warrant recommending its use. General supportive measures and treatment of specific symptoms should be followed in all cases of overdosage.

11 DESCRIPTION

Tacrolimus, previously known as FK506, is the active ingredient in PROGRAF. Tacrolimus is a calcineurin-inhibitor immunosuppressant produced by Streptomyces tsukubaensis. Chemically, tacrolimus is designated as [3S-[3R*[E(1S*,3S*,4S*)], 4S*,5R*,8S*,9E,12R*,14R*,15S*,16R*,18S*,19S*,26aR*]] -5,6,8,11,12,13,14,15,16,17,18,19,24,25,26,26a-hexadecahydro-5,19-dihydroxy-3-[2-(4-hydroxy-3-methoxycyclohexyl)-1-methylethenyl]-14,16-dimethoxy-4,10,12,18-tetramethyl-8-(2-propenyl)-15,19-epoxy-3H-pyrido[2,1-c][1,4] oxaazacyclotricosine-1,7,20,21(4H,23H)-tetrone, monohydrate.

The chemical structure of tacrolimus is:

Tacrolimus has an empirical formula of C44H69NO12•H2O and a formula weight of 822.03. Tacrolimus appears as white crystals or crystalline powder. It is practically insoluble in water, freely soluble in ethanol, and very soluble in methanol and chloroform.

PROGRAF is available for oral administration as capsules (tacrolimus capsules USP) containing the equivalent of 0.5 mg, 1 mg or 5 mg of anhydrous tacrolimus USP. Inactive ingredients include croscarmellose sodium NF, hypromellose USP, lactose monohydrate NF, and magnesium stearate NF. The 0.5 mg capsule shell contains ferric oxide NF, gelatin NF and titanium dioxide USP, the 1 mg capsule shell contains gelatin NF and titanium dioxide USP, and the 5 mg capsule shell contains ferric oxide NF, gelatin NF, and titanium dioxide USP.

PROGRAF is also available as a sterile solution (tacrolimus injection) containing the equivalent of 5 mg anhydrous tacrolimus USP in 1 mL for administration by intravenous infusion only. Each mL contains the following inactive ingredients: dehydrated alcohol USP, 80.0% v/v and polyoxyl 60 hydrogenated castor oil (HCO-60), 200 mg. PROGRAF injection must be diluted with 0.9% Sodium Chloride Injection or 5% Dextrose Injection before use.

PROGRAF Granules is available for oral administration as a suspension containing the equivalent of 0.2 mg or 1 mg of anhydrous tacrolimus USP. Inactive ingredients include croscarmellose sodium NF, hypromellose USP, and lactose monohydrate NF.

12 CLINICAL PHARMACOLOGY

12.1 Mechanism of Action

Tacrolimus binds to an intracellular protein, FKBP-12. A complex of tacrolimus-FKBP-12, calcium, calmodulin, and calcineurin (a ubiquitous mammalian intracellular enzyme) is then formed, after which the phosphatase activity of calcineurin is inhibited. Such inhibition prevents the dephosphorylation and translocation of various factors such as the nuclear factor of activated T-cells (NF-AT), and nuclear factor kappa-light-chain enhancer of activated B-cells (NF-κB).

Tacrolimus inhibits the expression and/or production of several cytokines that include interleukin (IL)-1 beta, IL-2, IL-3, IL-4, IL-5, IL-6, IL-8, IL-10, gamma interferon, tumor necrosis factor-alpha, and granulocyte macrophage colony-stimulating factor. Tacrolimus also inhibits IL-2 receptor expression and nitric oxide release, induces apoptosis and production of transforming growth factor beta that can lead to immunosuppressive activity. The net result is the inhibition of T-lymphocyte activation and proliferation, as well as T-helper-cell-dependent B-cell response (i.e., immunosuppression).

12.3 Pharmacokinetics

Tacrolimus activity is primarily due to the parent drug. The pharmacokinetic parameters (mean ± S.D.) of tacrolimus have been determined following intravenous (IV) and/or oral (PO) administration in healthy volunteers, and in kidney transplant, liver transplant, and heart transplant patients (Table 17).

Table 17. Pharmacokinetics Parameters (mean ± S.D.) of Tacrolimus in Healthy Volunteers and Patients
Population | N | Route (Dose) | Parameters
Population | N | Route (Dose) | Cmax (ng/mL) | Tmax (hr) | AUC (ng•hr/mL) | t1/2 (hr) | CL (L/hr/kg) | V (L/kg)
Healthy; Volunteers | 8 | IV (0.025 mg/kg/4 hr) | [Not applicable] |  | 652 [AUC0-inf] ± 156 | 34.2 ± 7.7 | 0.040 ± 0.009 | 1.91 ± 0.31
Healthy; Volunteers | 30 | PO (5 mg) (granules) | 35.6 ± 10.9 | 1.3 ± 0.5 | 320 ± 164 | 32.1 ± 5.9 | [Not available]
Healthy; Volunteers | 30 | PO (5 mg) (capsules) | 28.8 ± 8.9 | 1.5 ± 0.7 | 266 ± 95 | 32.3 ± 8.8
Kidney; Transplant; Patients | 26 | IV (0.02 mg/kg/12 hr) |  |  | 294 ± 262 | 18.8 ± 16.7 | 0.083 ± 0.050 | 1.41 ± 0.66
Kidney; Transplant; Patients | 26 | PO (0.2 mg/kg/day) | 19.2 ± 10.3 | 3.0 | 203 ± 42
Kidney; Transplant; Patients | 26 | PO (0.3 mg/kg/day) | 24.2 ± 15.8 | 1.5 | 288 ± 93
Liver; Transplant; Patients | 17 | IV (0.05 mg/kg/12 hr) |  |  | 3300 ± 2130 | 11.7 ± 3.9 | 0.053 ± 0.017 | 0.85 ± 0.30
Liver; Transplant; Patients | 17 | PO (0.3 mg/kg/day) | 68.5 ± 30.0 | 2.3 ± 1.5 | 519 ± 179
Heart; Transplant Patients | 11 | IV (0.01 mg/kg/day as a continuous infusion) |  |  | 954 [AUC0-t] ± 334 | 23.6 ± 9.22 | 0.051 ± 0.015
Heart; Transplant Patients | 11 | PO (0.075 mg/kg/day) [Determined after the first dose] | 14.7 ± 7.79 | 2.1 [0.5-6.0] [Median [range]] | 82.7 [AUC0-12] ± 63.2
Heart; Transplant Patients | 14 | PO (0.15 mg/kg/day) | 24.5 ± 13.7 | 1.5 [0.4-4.0] | 142 ± 116

Due to intersubject variability in tacrolimus pharmacokinetics, individualization of the dosing regimen is necessary for optimal therapy [see Dosage and Administration (2.6)]. Pharmacokinetic data indicate that whole blood concentrations rather than plasma concentrations serve as the more appropriate sampling compartment to describe tacrolimus pharmacokinetics.

Absorption

Absorption of tacrolimus from the gastrointestinal tract after oral administration is incomplete and variable. The absolute bioavailability of tacrolimus was 17 ± 10% in adult kidney transplant patients (N = 26), 22 ± 6% in adult liver transplant patients (N = 17), 23 ± 9% in adult heart transplant patients (N = 11) and 18 ± 5% in healthy volunteers (N = 16).

A single dose trial conducted in 32 healthy volunteers established the bioequivalence of the 1 mg and 5 mg capsules. Another single dose trial in 32 healthy volunteers established the bioequivalence of the 0.5 mg and 1 mg capsules. Tacrolimus maximum blood concentrations (Cmax) and area under the curve (AUC) appeared to increase in a dose-proportional fashion in 18 fasted healthy volunteers receiving a single oral dose of 3, 7, and 10 mg.

In 18 kidney transplant patients, tacrolimus trough concentrations from 3 to 30 ng/mL measured at 10-12 hours post-dose (Cmin) correlated well with the AUC (correlation coefficient 0.93). In 24 liver transplant patients over a concentration range of 10 to 60 ng/mL, the correlation coefficient was 0.94. In 25 heart transplant patients over a concentration range of 2 to 24 ng/mL, the correlation coefficient was 0.89 after an oral dose of 0.075 or 0.15 mg/kg/day at steady-state.

In a healthy volunteer adult study, the systemic exposure to tacrolimus (AUC) for PROGRAF Granules was approximately 16% higher than that for PROGRAF capsules when administered as single doses. If pediatric patients are converted between formulations, therapeutic drug monitoring must be performed and dose adjustments made to ensure that systemic exposure to tacrolimus is maintained.

Food Effects

The rate and extent of tacrolimus absorption were greatest under fasted conditions. The presence and composition of food decreased both the rate and extent of tacrolimus absorption when administered to 15 healthy volunteers.

The effect was most pronounced with a high-fat meal (848 kcal, 46% fat): mean AUC and Cmax were decreased 37% and 77%, respectively; Tmax was lengthened 5-fold. A high-carbohydrate meal (668 kcal, 85% carbohydrate) decreased mean AUC and mean Cmax by 28% and 65%, respectively.

In healthy volunteers (N = 16), the time of the meal also affected tacrolimus bioavailability. When given immediately following the meal, mean Cmax was reduced 71%, and mean AUC was reduced 39%, relative to the fasted condition. When administered 1.5 hours following the meal, mean Cmax was reduced 63%, and mean AUC was reduced 39%, relative to the fasted condition.

In 11 liver transplant patients, PROGRAF administered 15 minutes after a high fat (400 kcal, 34% fat) breakfast, resulted in decreased AUC (27 ± 18%) and Cmax (50 ± 19%), as compared to a fasted state.

PROGRAF capsules should be taken consistently every day either with or without food because the presence and composition of food decreases the bioavailability of PROGRAF [see Dosage and Administration (2.1)].

Distribution

The plasma protein binding of tacrolimus is approximately 99% and is independent of concentration over a range of 5‑50 ng/mL. Tacrolimus is bound mainly to albumin and alpha-1-acid glycoprotein, and has a high level of association with erythrocytes. The distribution of tacrolimus between whole blood and plasma depends on several factors, such as hematocrit, temperature at the time of plasma separation, drug concentration, and plasma protein concentration. In a U.S. trial, the ratio of whole blood concentration to plasma concentration averaged 35 (range 12 to 67).

Elimination

Metabolism

Tacrolimus is extensively metabolized by the mixed-function oxidase system, primarily the cytochrome P-450 system (CYP3A4 and CYP3A5). A metabolic pathway leading to the formation of 8 possible metabolites has been proposed. Demethylation and hydroxylation were identified as the primary mechanisms of biotransformation in vitro. The major metabolite identified in incubations with human liver microsomes is 13-demethyl tacrolimus. In in vitro studies, a 31‑demethyl metabolite has been reported to have the same activity as tacrolimus.

Excretion

The mean clearance following IV administration of tacrolimus is 0.040, 0.083, 0.053, and 0.051 L/hr/kg in healthy volunteers, adult kidney transplant patients, adult liver transplant patients, and adult heart transplant patients, respectively. In man, less than 1% of the dose administered is excreted unchanged in urine.

In a mass balance study of IV-administered radiolabeled tacrolimus to 6 healthy volunteers, the mean recovery of radiolabel was 77.8 ± 12.7%. Fecal elimination accounted for 92.4 ± 1.0% and the elimination half-life based on radioactivity was 48.1 ± 15.9 hours whereas it was 43.5 ± 11.6 hours based on tacrolimus concentrations. The mean clearance of radiolabel was 0.029 ± 0.015 L/hr/kg and clearance of tacrolimus was 0.029 ± 0.009 L/hr/kg. When administered PO, the mean recovery of the radiolabel was 94.9 ± 30.7%. Fecal elimination accounted for 92.6 ± 30.7%, urinary elimination accounted for 2.3 ± 1.1% and the elimination half-life based on radioactivity was 31.9 ± 10.5 hours whereas it was 48.4 ± 12.3 hours based on tacrolimus concentrations. The mean clearance of radiolabel was 0.226 ± 0.116 L/hr/kg and clearance of tacrolimus was 0.172 ± 0.088 L/hr/kg.

Specific Populations

Pediatric Patients

PROGRAF capsules Pharmacokinetics in Pediatric Patients

Pharmacokinetics of tacrolimus have been studied in liver transplantation patients, 0.7 to 13.2 years of age. Following IV administration of a 0.037 mg/kg/day dose to 12 pediatric patients, mean terminal half-life, volume of distribution and clearance were 11.5 ± 3.8 hours, 2.6 ± 2.1 L/kg and 0.138 ± 0.071 L/hr/kg, respectively. Following oral administration to 9 patients, mean AUC and Cmax were 337 ± 167 ng·hr/mL and 48.4 ± 27.9 ng/mL, respectively. The absolute bioavailability was 31 ± 24%.

Pharmacokinetics of tacrolimus have also been studied in kidney transplantation patients, 8.2 ± 2.4 years of age. Following IV infusion of a 0.06 mg/kg/day to 12 pediatric patients (8 male and 4 female), mean terminal half-life and clearance were 10.2 ± 5.0 hours and 0.12 ± 0.04 L/hr/kg, respectively. Following oral administration to the same patients, mean AUC and Cmax were 181 ± 65 ng·hr/mL and 30 ± 11 ng/mL, respectively. The absolute bioavailability was 19 ± 14%.

Whole blood trough concentrations from 31 patients less than 12 years old showed that pediatric patients needed higher doses than adults to achieve similar tacrolimus trough concentrations [see Dosage and Administration (2.3)].

PROGRAF Granules Pharmacokinetics in Pediatric Patients

A multicenter, open-label, single arm, pharmacokinetic study (OPTION, NCT01371331) was conducted using tacrolimus granules for oral suspension in pediatric patients undergoing de novo liver, kidney, or heart transplant. After an initial 24‑hour continuous IV infusion of tacrolimus (0.025 mg/kg/hour) for 12 hours to 4 days, oral PROGRAF Granules were dosed at 0.3 mg/kg/day in divided doses twice daily. Tacrolimus whole blood trough concentrations ranged from 5‑15 ng/mL for the first month post-transplant, and 5-10 ng/mL thereafter. Two pharmacokinetic (PK) profiles, AUC, Cmax, Tmax and Ctrough, were taken after the first oral dose (Day 1) and at steady state (Day 7). Subsequent oral doses of PROGRAF Granules were adjusted based on clinical evidence of efficacy, the whole-blood trough levels, and/or occurrence of adverse events. Of 52 patients enrolled, thirty-eight (38) had an evaluable PK profile. The mean pediatric age was 6.1 years for heart transplant, 1.1 years for liver transplant and 3.6 years for kidney transplant. Summary results of PK parameters are presented in Table 18.

Table 18. Summary of Whole Blood PK Parameters of Tacrolimus after Administration of PROGRAF Granules in Pediatric Patients
Population | N; (age range) |  | Parameters
Population | N; (age range) |  | AUCtau [hr*ng/mL]; mean ± SD | Cmax [ng/mL]; mean ± SD | Tmax [hr]; mean ± SD | Ctrough [ng/mL]; mean ± SD
Heart Transplant Patients | 12; (0.58-13 years) | Day 1; Day 7 | 224.13 ± 114.30; 165.17 ± 39.12 | 45.61 ± 19.55; 32.69 ± 9.78 | 2.95 ± 4.33; 0.84 ± 0.44 | 12.60 ± 13.40; 7.57 ± 1.80
Liver Transplant Patients | 14; (0.33-12 years) | Day 1; Day 7 | 210.56 ± 84.01; 195.08 ± 94.63 | 25.11 ± 10.78; 30.52 ± 19.35 | 2.73 ± 1.84; 1.71 ± 1.12 | 13.41 ± 7.11; 9.71 ± 4.03
Kidney Transplant Patients | 12; (2.42-11 years) | Day 1; Day 7 | 97.40 ± 36.77; 208.32 ± 68.75 | 18.04 ± 8.10; 36.63 ± 13.97 | 1.78 ± 0.88; 1.09 ± 0.61 | 3.54 ± 1.45; 8.92 ± 3.59

Renal and Hepatic Impaired Patients

The mean pharmacokinetic parameters for tacrolimus following single administrations to adult patients with renal and hepatic impairment are given in Table 19.

Table 19. Pharmacokinetics in Renal and Hepatic Impaired Adult Patients
Population; (No. of Patients) | Dose | AUC0-t; (ng·hr/mL) | t1/2; (hr) | V; (L/kg) | CI; (L/hr/kg)
Renal; Impairment; (n = 12) | 0.02; mg/kg/4 hr; IV | 393 ± 123; (t = 60 hr) | 26.3 ± 9.2 | 1.07 ± 0.20 | 0.038 ± 0.014
Mild Hepatic; Impairment; (n = 6) | 0.02; mg/kg/4 hr; IV | 367 ± 107; (t = 72 hr) | 60.6 ± 43.8; Range: 27.8 – 141 | 3.1 ± 1.6 | 0.042 ± 0.02
Mild Hepatic; Impairment; (n = 6) | 7.7 mg; PO | 488 ± 320; (t = 72 hr) | 66.1 ± 44.8; Range: 29.5 – 138 | 3.7 ± 4.7 [Corrected for bioavailability] | 0.034 ± 0.019
Severe; Hepatic; Impairment; (n = 6, IV) | 0.02 mg/kg/4 hr; IV (n = 2) 0.01 mg/kg/8 hr; IV (n = 4) | 762 ± 204; (t = 120 hr) 289 ± 117; (t = 144 hr) | 198 ± 158; Range: 81 – 436 | 3.9 ± 1.0 | 0.017 ± 0.013
(n = 5, PO) [1 patient did not receive the PO dose] | 8 mg PO; (n = 1) 5 mg PO; (n = 4); 4 mg PO; (n = 1) | 658; (t = 120 hr) 533 ± 156; (t = 144 hr) | 119 ± 35; Range: 85 – 178 | 3.1 ± 3.4 | 0.016 ± 0.011

Patients with Renal Impairment

Tacrolimus pharmacokinetics, following a single IV administration, were determined in 12 patients (7 not on dialysis and 5 on dialysis, serum creatinine of 3.9 ± 1.6 and 12.0 ± 2.4 mg/dL, respectively) prior to their kidney transplant. The pharmacokinetic parameters obtained were similar for both groups. The mean clearance of tacrolimus in patients with renal dysfunction was similar to that in normal volunteers (Table 19) [see Dosage and Administration (2.2) and Use in Specific Populations (8.6)].

Patients with Hepatic Impairment

Tacrolimus pharmacokinetics have been determined in six patients with mild hepatic dysfunction (mean Pugh score: 6.2) following single IV and oral administrations. The mean clearance of tacrolimus in patients with mild hepatic dysfunction was not substantially different from that in normal volunteers (see previous table). Tacrolimus pharmacokinetics were studied in 6 patients with severe hepatic dysfunction (mean Pugh score: > 10). The mean clearance was substantially lower in patients with severe hepatic dysfunction, irrespective of the route of administration [see Dosage and Administration (2.5) and Use in Specific Populations (8.7)].

Patients with Cystic Fibrosis

Lower bioavailability of tacrolimus has been reported in patients with cystic fibrosis [see Dosage and Administration (2.2, 2.3)].

Racial or Ethnic Groups

The pharmacokinetics of tacrolimus have been studied following single IV and oral administration of PROGRAF to 10 African-American, 12 Latino-American, and 12 Caucasian healthy volunteers. There were no significant pharmacokinetic differences among the three ethnic groups following a 4-hour IV infusion of 0.015 mg/kg. However, after single oral administration of 5 mg, mean (± SD) tacrolimus Cmax in African-Americans (23.6 ± 12.1 ng/mL) was significantly lower than in Caucasians (40.2 ± 12.6 ng/mL) and the Latino-Americans (36.2 ± 15.8 ng/mL) (p < 0.01). Mean AUC0-inf tended to be lower in African-Americans (203 ± 115 ng·hr/mL) than Caucasians (344 ± 186 ng·hr/mL) and Latino-Americans (274 ± 150 ng·hr/mL). The mean (± SD) absolute oral bioavailability (F) in African-Americans (12 ± 4.5%) and Latino-Americans (14 ± 7.4%) was significantly lower than in Caucasians (19 ± 5.8%, p = 0.011). There was no significant difference in mean terminal T1/2 among the three ethnic groups (range from approximately 25 to 30 hours). A retrospective comparison of African-American and Caucasian kidney transplant patients indicated that African-American patients required higher tacrolimus doses to attain similar trough concentrations [see Dosage and Administration (2.2)].

Male and Female Patients

A formal trial to evaluate the effect of gender on tacrolimus pharmacokinetics has not been conducted, however, there was no difference in dosing by gender in the kidney transplant trial. A retrospective comparison of pharmacokinetics in healthy volunteers, and in kidney, liver, and heart transplant patients indicated no gender-based differences.

Drug Interaction Studies

Frequent monitoring of whole blood concentrations and appropriate dosage adjustments of tacrolimus are recommended when concomitant use of the following drugs with tacrolimus is initiated or discontinued [see Drug Interactions (7)].

- Telaprevir: In a single-dose study in 9 healthy volunteers, co-administration of tacrolimus (0.5 mg single dose) with telaprevir (750 mg three times daily for 13 days) increased the tacrolimus dose-normalized Cmax by 9.3-fold and AUC by 70-fold compared to tacrolimus alone [see Drug Interactions (7.2)].
- Boceprevir: In a single-dose study in 12 subjects, co-administration of tacrolimus (0.5 mg single dose) with boceprevir (800 mg three times daily for 11 days) increased tacrolimus Cmax by 9.9-fold and AUC by 17-fold compared to tacrolimus alone [see Drug Interactions (7.2)].
- Nelfinavir: Based on a clinical study of 5 liver transplant recipients, co-administration of tacrolimus with nelfinavir increased blood concentrations of tacrolimus significantly and, as a result, a reduction in the tacrolimus dose by an average of 16-fold was needed to maintain mean trough tacrolimus blood concentrations of 9.7 ng/mL. It is recommended to avoid concomitant use of PROGRAF and nelfinavir unless the benefits outweigh the risks [see Drug Interactions (7.2)].
- Rifampin: In a study of 6 normal volunteers, a significant decrease in tacrolimus oral bioavailability (14 ± 6% vs. 7 ± 3%) was observed with concomitant rifampin administration (600 mg). In addition, there was a significant increase in tacrolimus clearance (0.036 ± 0.008 L/hr/kg vs. 0.053 ± 0.010 L/hr/kg) with concomitant rifampin administration [see Drug Interactions (7.2)].
- Magnesium and Aluminum-hydroxide: In a single-dose crossover study in healthy volunteers, co-administration of tacrolimus and magnesium-aluminum-hydroxide resulted in a 21% increase in the mean tacrolimus AUC and a 10% decrease in the mean tacrolimus Cmax relative to tacrolimus administration alone [see Drug Interactions (7.2)].
- Ketoconazole: In a study of 6 normal volunteers, a significant increase in tacrolimus oral bioavailability (14 ± 5% vs. 30 ± 8%) was observed with concomitant ketoconazole administration (200 mg). The apparent oral clearance of tacrolimus during ketoconazole administration was significantly decreased compared to tacrolimus alone (0.430 ± 0.129 L/hr/kg vs. 0.148 ± 0.043 L/hr/kg). Overall, IV clearance of tacrolimus was not significantly changed by ketoconazole co-administration, although it was highly variable between patients [see Drug Interactions (7.2)].
- Voriconazole (see complete prescribing information for VFEND): Repeat oral dose administration of voriconazole (400 mg every 12 hours for one day, then 200 mg every 12 hours for 6 days) increased tacrolimus (0.1 mg/kg single dose) Cmax and AUCτ in healthy subjects by an average of 2-fold (90% CI: 1.9, 2.5) and 3-fold (90% CI: 2.7, 3.8), respectively [see Drug Interactions (7.2)].
- Posaconazole (see complete prescribing information for Noxafil): Repeat oral administration of posaconazole (400 mg twice daily for 7 days) increased tacrolimus (0.05 mg/kg single dose) Cmax and AUC in healthy subjects by an average of 2-fold (90% CI: 2.01, 2.42) and 4.5-fold (90% CI 4.03, 5.19), respectively [see Drug Interactions (7.2)].
- Caspofungin (see complete prescribing information for CANCIDAS): Caspofungin reduced the blood AUC0-12 of tacrolimus by approximately 20%, peak blood concentration (Cmax) by 16%, and 12-hour blood concentration (C12hr) by 26% in healthy adult subjects when tacrolimus (2 doses of 0.1 mg/kg 12 hours apart) was administered on the 10th day of CANCIDAS 70 mg daily, as compared to results from a control period in which tacrolimus was administered alone [see Drug Interactions (7.2)]. The mechanism of interaction has not been confirmed.

13 NONCLINICAL TOXICOLOGY

13.1 Carcinogenesis, Mutagenesis, Impairment of Fertility

Carcinogenesis

Carcinogenicity studies were conducted in male and female rats and mice. In the 80-week mouse oral study and in the 104-week rat oral study, no relationship of tumor incidence to tacrolimus dosage was found. The highest dose used in the mouse was 3.0 mg/kg/day (0.9 to 2.2 times the AUC at clinical doses of 0.075 to 0.2 mg/kg/day) and in the rat was 5.0 mg/kg/day (0.265 to 0.65 times the AUC at clinical doses of 0.075 to 0.2 mg/kg/day) [see Warnings and Precautions (5.1)].

A 104-week dermal carcinogenicity study was performed in mice with tacrolimus ointment (0.03% - 3%), equivalent to tacrolimus doses of 1.1-118 mg/kg/day or 3.3-354 mg/m^2/day. In the study, the incidence of skin tumors was minimal and the topical application of tacrolimus was not associated with skin tumor formation under ambient room lighting. However, a statistically significant elevation in the incidence of pleomorphic lymphoma in high-dose male (25/50) and female animals (27/50) and in the incidence of undifferentiated lymphoma in high-dose female animals (13/50) was noted in the mouse dermal carcinogenicity study. Lymphomas were noted in the mouse dermal carcinogenicity study at a daily dose of 3.5 mg/kg (0.1% tacrolimus ointment). No drug-related tumors were noted in the mouse dermal carcinogenicity study at a daily dose of 1.1 mg/kg (0.03% tacrolimus ointment). The relevance of topical administration of tacrolimus in the setting of systemic tacrolimus use is unknown.

The implications of these carcinogenicity studies to the human condition are limited; doses of tacrolimus were administered that likely induced immunosuppression in these animals, impairing their immune system’s ability to inhibit unrelated carcinogenesis.

Mutagenesis

No evidence of genotoxicity was seen in bacterial (Salmonella and E. coli) or mammalian (Chinese hamster lung-derived cells) in vitro assays of mutagenicity, the in vitro CHO/HGPRT assay of mutagenicity, or in vivo clastogenicity assays performed in mice; tacrolimus did not cause unscheduled DNA synthesis in rodent hepatocytes.

Impairment of Fertility

Tacrolimus, subcutaneously administered to male rats at paternally toxic doses of 2 mg/kg/day (1.6 to 4.3 times the recommended clinical dose range [0.2 to 0.075 mg/kg/day] on a mg/m^2 basis) or 3 mg/kg/day (2.4 to 6.4 times the recommended clinical dose range), resulted in a dose-related decrease in sperm count. Tacrolimus, administered orally at 1.0 mg/kg (0.8 to 2.2 times the clinical dose range) to male and female rats, prior to and during mating, as well as to dams during gestation and lactation, was associated with embryolethality and adverse effects on female reproduction. Effects on female reproductive function (parturition) and embryolethal effects were indicated by a higher rate of pre- and post-implantation loss and increased numbers of undelivered and nonviable pups. When administered at 3.2 mg/kg (2.6 to 6.9 times the clinical dose range based on body surface area), tacrolimus was associated with maternal and paternal toxicity as well as reproductive toxicity including marked adverse effects on estrus cycles, parturition, pup viability, and pup malformations.

14 CLINICAL STUDIES

14.1 Kidney Transplantation

PROGRAF/Azathioprine (AZA)

PROGRAF-based immunosuppression in conjunction with azathioprine and corticosteroids following kidney transplantation was assessed in a randomized, multicenter, non-blinded, prospective trial. There were 412 kidney transplant patients enrolled at 19 clinical sites in the United States. Study therapy was initiated when renal function was stable as indicated by a serum creatinine ≤ 4 mg/dL (median of 4 days after transplantation, range 1 to 14 days). Patients less than 6 years of age were excluded.

There were 205 patients randomized to PROGRAF-based immunosuppression and 207 patients were randomized to cyclosporine-based immunosuppression. All patients received prophylactic induction therapy consisting of an antilymphocyte antibody preparation, corticosteroids, and azathioprine. Overall, 1-year patient and graft survivals were 96.1% and 89.6%, respectively.

Data from this trial of PROGRAF in conjunction with azathioprine indicate that during the first 3 months of that trial, 80% of the patients maintained trough concentrations between 7-20 ng/mL, and then between 5-15 ng/mL, through 1 year.

PROGRAF/Mycophenolate Mofetil (MMF)

PROGRAF-based immunosuppression in conjunction with MMF, corticosteroids, and induction has been studied. In a randomized, open-label, multicenter trial (Study 1), 1589 kidney transplant patients received PROGRAF (Group C, n = 401), sirolimus (Group D, n = 399), or one of two cyclosporine (CsA) regimens (Group A, n = 390 and Group B, n = 399) in combination with MMF and corticosteroids; all patients, except those in one of the two cyclosporine groups, also received induction with daclizumab. The trial was conducted outside the United States; the trial population was 93% Caucasian. In this trial, mortality at 12 months in patients receiving PROGRAF/MMF was similar (3%) compared to patients receiving cyclosporine/MMF (3% and 2%) or sirolimus/MMF (3%). Patients in the PROGRAF group exhibited higher estimated creatinine clearance rates (eCLcr) using the Cockcroft-Gault formula (Table 20) and experienced fewer efficacy failures, defined as biopsy-proven acute rejection (BPAR), graft loss, death, and/or loss to follow-up (Table 21) in comparison to each of the other three groups. Patients randomized to PROGRAF/MMF were more likely to develop diarrhea and diabetes after the transplantation and experienced similar rates of infections compared to patients randomized to either cyclosporine/MMF regimen [see Adverse Reactions (6.1)].

Table 20. Estimated Creatinine Clearance at 12 Months (Study 1)
Group | eCLcr [mL/min] at Month 12 [All death/graft loss (n = 41, 27, 23, and 42 in Groups A, B, C, and D) and patients whose last recorded creatinine values were prior to month 3 visit (n = 10, 9, 7, and 9 in Groups A, B, C, and D, respectively) were imputed with Glomerular Filtration Rate (GFR) of 10 mL/min; a subject's last observed creatinine value from month 3 on was used for the remainder of subjects with missing creatinine at month 12 (n = 11, 12, 15, and 19 for Groups A, B, C, and D, respectively). Weight was also imputed in the calculation of estimated GFR, if missing.]
Group | N | MEAN | SD | MEDIAN | Treatment Difference with Group C (99.2% CI [Adjusted for multiple (6) pairwise comparisons using Bonferroni corrections.])
(A) CsA/MMF/CS | 390 | 56.5 | 25.8 | 56.9 | -8.6 (-13.7, -3.7)
(B) CsA/MMF/CS/Daclizumab | 399 | 58.9 | 25.6 | 60.9 | -6.2 (-11.2, -1.2)
(C) Tac/MMF/CS/Daclizumab | 401 | 65.1 | 27.4 | 66.2 | -
(D) Siro/MMF/CS/Daclizumab | 399 | 56.2 | 27.4 | 57.3 | -8.9 (-14.1, -3.9)
Total | 1589 | 59.2 | 26.8 | 60.5
Key: CsA = Cyclosporine, CS = Corticosteroids, Tac = Tacrolimus, Siro = Sirolimus

Table 21. Incidence of BPAR, Graft Loss, Death, or Loss to Follow-up at 12 Months (Study 1)
 | Group A N = 390 | Group B N = 399 | Group C N = 401 | Group D N = 399
Overall Failure | 141 (36.2%) | 126 (31.6%) | 82 (20.4%) | 185 (46.4%)
Components of efficacy failure
BPAR | 113 (29.0%) | 106 (26.6%) | 60 (15.0%) | 152 (38.1%)
Graft loss excluding death | 28 (7.2%) | 20 (5.0%) | 12 (3.0%) | 30 (7.5%)
Mortality | 13 (3.3%) | 7 (1.8%) | 11 (2.7%) | 12 (3.0%)
Lost to follow-up | 5 (1.3%) | 7 (1.8%) | 5 (1.3%) | 6 (1.5%)
Treatment Difference of efficacy failure compared to Group C (99.2% CI [Adjusted for multiple (6) pairwise comparisons using Bonferroni corrections.]) | 15.8%; (7.1%, 24.3%) | 11.2%; (2.7%, 19.5%) | - | 26.0%; (17.2%, 34.7%)
Key: Group A = CsA/MMF/CS, B = CsA/MMF/CS/Daclizumab, C = Tac/MMF/CS/Daclizumab, and D = Siro/MMF/CS/Daclizumab

The protocol-specified target tacrolimus trough concentrations (Ctrough,Tac) were 3-7 ng/mL; however, the observed median Ctroughs,Tac approximated 7 ng/mL throughout the 12-month trial (Table 22). Approximately 80% of patients maintained tacrolimus whole blood concentrations between 4-11 ng/mL through 1 year post-transplant.

Table 22. Tacrolimus Whole Blood Trough Concentration Range (Study 1)
Time | Median (P10-P90 [10 to 90th Percentile: range of Ctrough,Tac that excludes lowest 10% and highest 10% of Ctrough,Tac]) tacrolimus whole blood trough concentration range (ng/mL)
Day 30 (N = 366) | 6.9 (4.4 – 11.3)
Day 90 (N = 351) | 6.8 (4.1 – 10.7)
Day 180 (N = 355) | 6.5 (4.0 – 9.6)
Day 365 (N = 346) | 6.5 (3.8 – 10.0)

The protocol-specified target cyclosporine trough concentrations (Ctrough,CsA) for Group B were 50-100 ng/mL; however, the observed median Ctroughs,CsA approximated 100 ng/mL throughout the 12-month trial. The protocol-specified target Ctroughs,CsA for Group A were 150-300 ng/mL for the first 3 months and 100-200 ng/mL from month 4 to month 12; the observed median Ctroughs,CsA approximated 225 ng/mL for the first 3 months and 140 ng/mL from month 4 to month 12.

While patients in all groups started MMF at 1 gram twice daily, the MMF dose was reduced to less than 2 g per day in 63% of patients in the tacrolimus treatment arm by month 12 (Table 23); approximately 50% of these MMF dose reductions were due to adverse reactions. By comparison, the MMF dose was reduced to less than 2 g per day in 49% and 45% of patients in the two cyclosporine arms (Group A and Group B, respectively), by month 12 and approximately 40% of MMF dose reductions were due to adverse reactions.

Table 23. MMF Dose Over Time in PROGRAF/MMF (Group C) (Study 1)
Time period (Days) | Time-averaged MMF dose (grams per day) [Percentage of patients for each time-averaged MMF dose range during various treatment periods. Administration of 2 g per day of time-averaged MMF dose means that MMF dose was not reduced in those patients during the treatment periods.]
Time period (Days) | Less than 2.0 | 2.0 | Greater than 2.0
0-30 (N = 364) | 37% | 60% | 2%
0-90 (N = 373) | 47% | 51% | 2%
0-180 (N = 377) | 56% | 42% | 2%
0-365 (N = 380) | 63% | 36% | 1%
Key: Time-averaged MMF dose = (total MMF dose)/(duration of treatment)

In a second randomized, open-label, multicenter trial (Study 2), 424 kidney transplant patients received PROGRAF (N = 212) or cyclosporine (N = 212) in combination with MMF 1 gram twice daily, basiliximab induction, and corticosteroids. In this trial, the rate for the combined endpoint of BPAR, graft failure, death, and/or lost to follow-up at 12 months in the PROGRAF/MMF group was similar to the rate in the cyclosporine/MMF group. There was, however, an imbalance in mortality at 12 months in those patients receiving PROGRAF/MMF (4%) compared to those receiving cyclosporine/MMF (2%), including cases attributed to over-immunosuppression (Table 24).

Table 24. Incidence of BPAR, Graft Loss, Death, or Loss to Follow-up at 12 Months (Study 2)
 | PROGRAF/MMF | Cyclosporine/MMF
 | (N = 212) | (N = 212)
Overall Failure | 32 (15.1%) | 36 (17.0%)
Components of efficacy failure
BPAR | 16 (7.5%) | 29 (13.7%)
Graft loss excluding death | 6 (2.8%) | 4 (1.9%)
Mortality | 9 (4.2%) | 5 (2.4%)
Lost to follow-up | 4 (1.9%) | 1 (0.5%)
Treatment Difference of efficacy failure compared to PROGRAF/MMF group (95% CI [95% confidence interval calculated using Fisher's Exact Test.]) |  | 1.9% (-5.2%, 9.0%)

The protocol-specified target tacrolimus whole blood trough concentrations (Ctrough,Tac) in Study 2 were 7-16 ng/mL for the first three months and 5-15 ng/mL thereafter. The observed median Ctroughs,Tac approximated 10 ng/mL during the first three months and 8 ng/mL from month 4 to month 12 (Table 25). Approximately 80% of patients maintained tacrolimus whole blood trough concentrations between 6 to 16 ng/mL during months 1 through 3 and, then, between 5 to 12 ng/mL from month 4 through 1 year.

Table 25. Tacrolimus Whole Blood Trough Concentration Range (Study 2)
Time | Median (P10-P90 [10 to 90th Percentile: range of Ctrough,Tac that excludes lowest 10% and highest 10% of Ctrough,Tac.]) tacrolimus whole blood trough concentration range (ng/mL)
Day 30 (N = 174) | 10.5 (6.3 – 16.8)
Day 60 (N = 179) | 9.2 (5.9 – 15.3)
Day 120 (N = 176) | 8.3 (4.6 – 13.3)
Day 180 (N = 171) | 7.8 (5.5 – 13.2)
Day 365 (N = 178) | 7.1 (4.2 – 12.4)

The protocol-specified target cyclosporine whole blood concentrations (Ctrough,CsA) were 125 to 400 ng/mL for the first three months, and 100 to 300 ng/mL thereafter. The observed median Ctroughs,CsA approximated 280 ng/mL during the first three months and 190 ng/mL from month 4 to month 12.

Patients in both groups started MMF at 1 gram twice daily. The MMF dose was reduced to less than 2 grams per day by month 12 in 62% of patients in the PROGRAF/MMF group (Table 26) and in 47% of patients in the cyclosporine/MMF group. Approximately 63% and 55% of these MMF dose reductions were because of adverse reactions in the PROGRAF/MMF group and the cyclosporine/MMF group, respectively [see Adverse Reactions (6.1)].

Table 26. MMF Dose Over Time in the PROGRAF/MMF Group (Study 2)
Time period (Days) | Time-averaged MMF dose (g/day) [Percentage of patients for each time-averaged MMF dose range during various treatment periods. Two grams per day of time-averaged MMF dose means that the MMF dose was not reduced in those patients during the treatment periods.]
Time period (Days) | Less than 2.0 | 2.0 | Greater than 2.0
0-30 (N = 212) | 25% | 69% | 6%
0-90 (N = 212) | 41% | 53% | 6%
0-180 (N = 212) | 52% | 41% | 7%
0-365 (N = 212) | 62% | 34% | 4%
Key: Time-averaged MMF dose = (total MMF dose)/(duration of treatment)

14.2 Liver Transplantation

The safety and efficacy of PROGRAF-based immunosuppression following orthotopic liver transplantation were assessed in two prospective, randomized, non-blinded multicenter trials. The active control groups were treated with a cyclosporine-based immunosuppressive regimen (CsA/AZA). Both trials used concomitant adrenal corticosteroids as part of the immunosuppressive regimens. These trials compared patient and graft survival rates at 12 months following transplantation.

In one trial, 529 patients were enrolled at 12 clinical sites in the United States; prior to surgery, 263 were randomized to the PROGRAF-based immunosuppressive regimen and 266 to the CsA/AZA. In 10 of the 12 sites, the same CsA/AZA protocol was used, while 2 sites used different control protocols. This trial excluded patients with renal dysfunction, fulminant hepatic failure with Stage IV encephalopathy, and cancers; pediatric patients (≤ 12 years old) were allowed.

In the second trial, 545 patients were enrolled at 8 clinical sites in Europe; prior to surgery, 270 were randomized to the PROGRAF-based immunosuppressive regimen and 275 to CsA/AZA. In this trial, each center used its local standard CsA/AZA protocol in the active-control arm. This trial excluded pediatric patients, but did allow enrollment of subjects with renal dysfunction, fulminant hepatic failure in Stage IV encephalopathy, and cancers other than primary hepatic with metastases.

One-year patient survival and graft survival in the PROGRAF-based treatment groups were similar to those in the CsA/AZA treatment groups in both trials. The overall 1-year patient survival (CsA/AZA and PROGRAF-based treatment groups combined) was 88% in the U.S. trial and 78% in the European trial. The overall 1-year graft survival (CsA/AZA and PROGRAF-based treatment groups combined) was 81% in the U.S. trial and 73% in the European trial. In both trials, the median time to convert from IV to oral PROGRAF dosing was 2 days.

Although there is a lack of direct correlation between tacrolimus concentrations and drug efficacy, data from clinical trials of liver transplant patients have shown an increasing incidence of adverse reactions with increasing trough blood concentrations. Most patients are stable when trough whole blood concentrations are maintained between 5 to 20 ng/mL. Long-term post-transplant patients are often maintained at the low end of this target range.

Data from the U.S. clinical trial show that the median trough blood concentrations, measured at intervals from the second week to one year post-transplantation, ranged from 9.8 ng/mL to 19.4 ng/mL.

Pediatric Liver Transplantation Using PROGRAF Granules

The efficacy and safety of PROGRAF Granules plus corticosteroids were compared with a triple regimen of cyclosporine/corticosteroids/azathioprine in a randomized, open-label study, in de novo pediatric liver transplant patients. The study was conducted outside the United States and enrolled patients aged 16 years or younger. The distribution of pediatric patients by age was similar in both treatment groups, with a majority < 5 years. Patients were randomized to either tacrolimus for oral suspension 0.3 mg/kg/day (N = 91) or cyclosporine 10 mg/kg/day orally (N = 90) initiated 6 hours after completion of transplant surgery. Doses throughout the 1-year study period were adjusted to maintain whole blood trough levels within 5-20 ng/mL [see Dosage and Administration (2.3)]. Based on trough levels, doses of tacrolimus were adjusted to 0.17 mg/kg/day and 0.14 mg/kg/day by days 2 and 3, respectively. At 12 months, the incidence rate of BPAR, graft loss, death, or loss to follow-up was 52.7% in the tacrolimus group and 61.1% in the cyclosporine group (Table 27).

Table 27. Key Efficacy Results at 12 Months in Pediatric Liver Transplant Recipients Receiving PROGRAF Granules or Cyclosporine
 | PROGRAF Granules (N = 91) | Cyclosporine (N = 90)
Overall Failure | 48 (52.7%) | 55 (61.1%)
Components of efficacy failure
BPAR | 40 (44.0%) | 49 (54.4%)
Graft loss | 7 (7.7%) | 13 (14.4%)
Graft loss excluding death | 1 (1.1%) | 6 (6.7%)
Mortality | 6 (6.6%) | 7 (7.8%)
Lost to follow-up | 2 (2.2%) | 0
Treatment Difference of efficacy failure compared to cyclosporine (95% CI [95% confidence interval calculated using normal approximation.]) | -8.4% (-22.7%, 6.0%)

14.3 Heart Transplantation

Two open-label, randomized, comparative trials evaluated the safety and efficacy of PROGRAF-based and cyclosporine-based immunosuppression in primary orthotopic heart transplantation. In a trial conducted in Europe, 314 patients received a regimen of antibody induction, corticosteroids, and azathioprine in combination with PROGRAF or cyclosporine modified for 18 months. In a 3-arm trial conducted in the U.S., 331 patients received corticosteroids and PROGRAF plus sirolimus, PROGRAF plus mycophenolate mofetil (MMF) or cyclosporine modified plus MMF for 1 year.

In the European trial, patient/graft survival at 18 months post-transplant was similar between treatment arms, 92% in the tacrolimus group and 90% in the cyclosporine group. In the U.S. trial, patient and graft survival at 12 months was similar with 93% survival in the PROGRAF plus MMF group and 86% survival in the cyclosporine modified plus MMF group. In the European trial, the cyclosporine trough concentrations were above the pre-defined target range (i.e., 100 to 200 ng/mL) at Day 122 and beyond in 32% to 68% of the patients in the cyclosporine treatment arm, whereas the tacrolimus trough concentrations were within the pre-defined target range (i.e., 5 to 15 ng/mL) in 74% to 86% of the patients in the tacrolimus treatment arm. Data from this European trial indicate that from 1 week to 3 months post-transplant, approximately 80% of patients maintained trough concentrations between 8 to 20 ng/mL and, from 3 months through 18 months post-transplant, approximately 80% of patients maintained trough concentrations between 6 to 18 ng/mL.

The U.S. trial contained a third arm of a combination regimen of sirolimus, 2 mg per day, and full-dose PROGRAF; however, this regimen was associated with increased risk of wound-healing complications, renal function impairment, and insulin-dependent post-transplant diabetes mellitus, and is not recommended [see Warnings and Precautions (5.10)].

14.4 Lung Transplantation

The efficacy and safety of PROGRAF-based immunosuppression in primary lung transplantation were assessed in a non-interventional (observational) study using data from the U.S. Scientific Registry of Transplant Recipients (SRTR). The study analyzed outcomes based on discharge immunosuppression treatment regimen in recipients of a primary lung transplant between 1999 and 2017 who were alive at the time of discharge. In adult patients receiving tacrolimus immediate-release products in combination with MMF (n=15,478) or tacrolimus immediate-release products in combination with AZA (n=4,263), the one-year graft survival estimates from time of discharge were 90.9% and 90.8%, respectively. In pediatric patients receiving tacrolimus immediate-release products in combination with MMF (n= 450) or tacrolimus immediate-release products in combination with AZA (n=72), the one-year graft survival estimates from time of discharge were 91.7% and 84.7%, respectively.

15 REFERENCES

1. “OSHA Hazardous Drugs.” OSHA. http://www.osha.gov/SLTC/hazardousdrugs/index.html

16 HOW SUPPLIED/STORAGE AND HANDLING

16.1 PROGRAF (tacrolimus) Capsules, USP

Strength | 0.5 mg; (containing the equivalent of 0.5 mg anhydrous tacrolimus USP) | 1 mg; (containing the equivalent of 1 mg anhydrous tacrolimus USP) | 5 mg; (containing the equivalent of 5 mg anhydrous tacrolimus USP)
Shape/color | oblong/light yellow | oblong/white | oblong/grayish red
Branding on; capsule cap/body | 607 | 617 | 657
100 count bottle | NDC 0469-0607-73 | NDC 0469-0617-73 | NDC 0469-0657-73

Note: PROGRAF capsules USP are not filled to maximum capsule capacity. Capsule contains labeled amount.

Store and Dispense

Store at 20°C to 25°C (68°F to 77°F); excursions permitted 15°C to 30°C (59°F to 86°F) [See USP Controlled Room Temperature].

16.2 PROGRAF (tacrolimus) Injection

(for Intravenous infusion only)

NDC 0469-3016-01 Product Code 301601

5 mg/mL (equivalent of 5 mg of anhydrous tacrolimus USP per mL) supplied as a sterile solution in a 1 mL ampule, in boxes of 10 ampules

Store and Dispense

Store between 5°C and 25°C (41°F and 77°F).

16.3 PROGRAF Granules (tacrolimus for oral suspension)

Strength | 0.2 mg; (containing the equivalent of 0.2 mg anhydrous tacrolimus USP) | 1 mg; (containing the equivalent of 1 mg anhydrous tacrolimus USP)
Shape/color | White granules | White granules
1 carton containing 50 packets | NDC 0469-1230-50 | NDC 0469-1330-50

Store and Dispense

Store at 20°C to 25°C (68°F to 77°F); excursions permitted 15°C to 30°C (59°F to 86°F) [See USP Controlled Room Temperature].

16.4 Handling and Disposal

Tacrolimus can cause fetal harm. PROGRAF capsules should not be opened or crushed. Wearing disposable gloves is recommended during dilution of the injection or when preparing the oral suspension in the hospital and when wiping any spills. Avoid inhalation or direct contact with skin or mucous membranes of the powder or granules contained in PROGRAF capsules and PROGRAF Granules, respectively. If such contact occurs, wash the skin thoroughly with soap and water; if ocular contact occurs, rinse eyes with water. In case a spill occurs, wipe the surface with a wet paper towel. Follow applicable special handling and disposal procedures^1.

17 PATIENT COUNSELING INFORMATION

Advise the patient to read the FDA-approved patient labeling (Patient Information and Instructions for Use).

17.1 Administration

Advise the patient or caregiver to:

- Inspect their PROGRAF medicine when they receive a new prescription and before taking it. If the appearance of the capsule is not the same as usual, or if dosage instructions have changed, advise patients to contact their healthcare provider as soon as possible to make sure that they have the right medicine. Other tacrolimus products cannot be substituted for PROGRAF.
- Take PROGRAF at the same 12-hour intervals every day to achieve consistent blood concentrations.
- Take PROGRAF consistently either with or without food because the presence and composition of food decreases the bioavailability of PROGRAF.
- Not to eat grapefruit or drink grapefruit juice in combination with PROGRAF [see Drug Interactions (7.2)].
- If the patient is receiving PROGRAF Granules, advise that the dose should be given immediately after preparation and not to save the dose for later. Advise the caregiver to carefully read the Instructions for Use.

17.2 Development of Lymphoma and Other Malignancies

Inform patients they are at increased risk of developing lymphomas and other malignancies, particularly of the skin, due to immunosuppression. Advise patients to limit exposure to sunlight and ultraviolet (UV) light by wearing protective clothing and using a broad spectrum sunscreen with a high protection factor [see Warnings and Precautions (5.1)].

17.3 Increased Risk of Infection

Inform patients they are at increased risk of developing a variety of infections, including opportunistic infections, due to immunosuppression and to contact their physician if they develop any symptoms of infection such as fever, sweats or chills, cough or flu-like symptoms, muscle aches, or warm, red, painful areas on the skin [see Warnings and Precautions (5.2)].

17.4 New Onset Diabetes After Transplant

Inform patients that PROGRAF can cause diabetes mellitus and should be advised to contact their physician if they develop frequent urination, increased thirst, or hunger [see Warnings and Precautions (5.4)].

17.5 Nephrotoxicity

Inform patients that PROGRAF can have toxic effects on the kidney that should be monitored. Advise patients to attend all visits and complete all blood tests ordered by their medical team [see Warnings and Precautions (5.5)].

17.6 Neurotoxicity

Inform patients that they are at risk of developing adverse neurologic reactions including seizure, altered mental status, and tremor. Advise patients to contact their physician should they develop vision changes, delirium, or tremors [see Warnings and Precautions (5.6)].

17.7 Hyperkalemia

Inform patients that PROGRAF can cause hyperkalemia. Monitoring of potassium levels may be necessary, especially with concomitant use of other drugs known to cause hyperkalemia [see Warnings and Precautions (5.7)].

17.8 Hypertension

Inform patients that PROGRAF can cause high blood pressure which may require treatment with antihypertensive therapy. Advise patients to monitor their blood pressure [see Warnings and Precautions (5.8)].

17.9 Thrombotic Microangiopathy

Inform patients that PROGRAF can cause blood clotting problems. The risk of this occurring increases when patients take PROGRAF and sirolimus or everolimus concomitantly, or when patients develop certain infections. Advise them to seek medical attention promptly if they develop fever, petequiae or bruises, fatigue, confusion, jaundice, oliguria. [see Warnings and Precautions (5.16)]

17.10 Drug Interactions

Instruct patients to tell their healthcare providers when they start or stop taking any medicines, including prescription medicines and nonprescription medicines, natural or herbal remedies, nutritional supplements, and vitamins. Advise patients to avoid grapefruit and grapefruit juice [see Drug Interactions (7)].

17.11 Pregnancy, Lactation and Infertility

Inform women of childbearing potential that PROGRAF can harm the fetus. Instruct male and female patients to discuss with their healthcare provider family planning options including appropriate contraception. Also, discuss with pregnant patients the risks and benefits of breastfeeding their infant [see Use in Specific Populations (8.1, 8.2, 8.3)].

Encourage female transplant patients who become pregnant and male patients who have fathered a pregnancy, exposed to immunosuppressants including tacrolimus, to enroll in the voluntary Transplantation Pregnancy Registry International. To enroll or register, patients can call the toll free number 1-877-955-6877 or https://www.transplantpregnancyregistry.org/ [see Use in Specific Populations (8.1)].

Based on animal studies, PROGRAF may affect fertility in males and females [see Nonclinical Toxicology (13.1)].

17.12 Myocardial Hypertrophy

Inform patients to report symptoms of tiredness, swelling, and/or shortness of breath (heart failure).

17.13 Immunizations

Inform patients that PROGRAF can interfere with the usual response to immunizations and that they should avoid live vaccines. [see Warnings and Precautions (5.14)].

Distributed by:
Astellas Pharma US, Inc.
Northbrook, IL 60062

PROGRAF® is a registered trademark of Astellas Pharma Inc. All other trademarks and registered trademarks are the property of their respective owners.

398977-PRG

Patient Information

PROGRAF® (PRO-graf) (tacrolimus) capsules, for oral use

PROGRAF® (PRO-graf) Granules (tacrolimus for oral suspension)

Read this Patient Information before you start taking PROGRAF and each time you get a refill. There may be new information. This information does not take the place of talking with your healthcare provider about your medical condition or your treatment.

What is the most important information I should know about PROGRAF?

PROGRAF can cause serious side effects, including:

- Increased risk of cancer. People who take PROGRAF have an increased risk of getting some kinds of cancer, including skin and lymph gland cancer (lymphoma).
- Increased risk of infection. PROGRAF is a medicine that affects your immune system. PROGRAF can lower the ability of your immune system to fight infections. Serious infections can happen in people receiving PROGRAF that can cause death. Call your healthcare provider right away if you have any symptoms of an infection, including:

- fever
- sweats or chills
- cough or flu-like symptoms

- muscle aches
- warm, red, or painful areas on your skin

What is PROGRAF?

- PROGRAF is a prescription medicine used with other medicines to help prevent organ rejection in people who have had a kidney, liver, heart, or lung transplant.
- PROGRAF capsules and PROGRAF GRANULES are types of tacrolimus immediate-release drugs and they are not the same as tacrolimus extended-release tablets or tacrolimus extended-release capsules. Your healthcare provider should decide what medicine is right for you.

Who should not take PROGRAF?

Do not take PROGRAF if you:

- are allergic to tacrolimus or any of the ingredients in PROGRAF. See the end of this leaflet for a complete list of ingredients in PROGRAF.

What should I tell my healthcare provider before taking PROGRAF?

Before taking PROGRAF, tell your healthcare provider about all of your medical conditions, including if you:

- plan to receive any vaccines. People taking PROGRAF should not receive live vaccines.
- have or have had liver, kidney, or heart problems.
- are pregnant or plan to become pregnant. PROGRAF can harm your unborn baby.
  - If you are able to become pregnant, you should use effective birth control before and during treatment with PROGRAF. Talk to your healthcare provider before starting treatment with PROGRAF about birth control methods that may be right for you.
  - Males who have female partners who are able to become pregnant should also use effective birth control before and during treatment with PROGRAF. Talk to your healthcare provider before starting treatment with PROGRAF about birth control methods that may be right for you.
  - There is a pregnancy registry for females who become pregnant and males who have fathered a pregnancy during treatment with PROGRAF. The purpose of this registry is to collect information about the health of you and your baby. To enroll in this voluntary registry, call 1-877-955-6877 or go to https://www.transplantpregnancyregistry.org/.
- are breastfeeding or plan to breastfeed. PROGRAF passes into your breast milk. You and your healthcare provider should decide if you will breastfeed while taking PROGRAF.
- plan to have children. PROGRAF may affect the ability to have children in females and males (fertility problems).

Tell your healthcare provider about all the medicines you take, and when you start a new medicine or stop taking a medicine, including prescription and over-the-counter medicines, vitamins, natural, herbal, or nutritional supplements.

Especially tell your healthcare provider if you take:

- sirolimus (RAPAMUNE): You should not take PROGRAF if you take sirolimus
- cyclosporine (GENGRAF, NEORAL, and SANDIMMUNE)
- medicines called aminoglycosides that are used to treat bacterial infections
- ganciclovir (CYTOVENE IV, VALCYTE)
- amphotericin B (ABELCET, AMBISOME)
- cisplatin
- antiviral medicines called nucleoside reverse transcriptase inhibitors
- antiviral medicines called protease inhibitors
- water pill (diuretic)
- medicine to treat high blood pressure
- nelfinavir (VIRACEPT)
- telaprevir (INCIVEK)
- boceprevir
- ritonavir (KALETRA, NORVIR, TECHNIVIE, VIEKIRA PAK, VIEKIRA XR)
- letermovir (PREVYMIS)
- ketoconazole
- itraconazole (ONMEL, SPORANOX)
- voriconazole (VFEND)
- caspofungin (CANCIDAS)
- clarithromycin (BIAXIN, BIAXIN XL, PREVPAC)
- rifampin (RIFADIN, RIFAMATE, RIFATER, RIMACTANE)
- rifabutin (MYCOBUTIN)
- amiodarone (NEXTERONE, PACERONE)
- cannabidiol (EPIDIOLEX)

Ask your healthcare provider or pharmacist if you are not sure if you take any of the medicines listed above.

PROGRAF may affect the way other medicines work, and other medicines may affect how PROGRAF works.

Know the medicines you take. Keep a list of your medicines and show it to your healthcare provider and pharmacist when you get a new medicine.

How should I take PROGRAF?

- Take PROGRAF exactly as your healthcare provider tells you to take it.
- Your healthcare provider will tell you how much PROGRAF to take and when to take it.
Your healthcare provider may change your PROGRAF dose if needed. Do not stop taking or change your dose of PROGRAF without talking to your healthcare provider.
- Take PROGRAF with or without food.
- Take PROGRAF the same way every day. For example, if you choose to take PROGRAF with food, you should always take PROGRAF with food.
- Take PROGRAF at the same time each day, 12 hours apart. For example, if you take your first dose at 7:00 a.m., you should take your second dose at 7:00 p.m.
- Taking PROGRAF at the same time each day helps to keep the amount of medicine in your body at a steady level.
- If you take too much PROGRAF, call your healthcare provider or go to the nearest hospital emergency room right away.

PROGRAF capsules:

- Do not open or crush PROGRAF capsules.

PROGRAF Granules:

- Children who have trouble swallowing capsules can be given PROGRAF Granules.
- Give the dose of PROGRAF Granules right after preparing. Do not save prepared PROGRAF Granules as a liquid to take at a later time.
- See the Instructions for Use at the end of this Patient Information for detailed instructions about how to mix and give PROGRAF Granules as a liquid in a glass cup or oral syringe.
- If you get the granules or prepared oral suspension on your skin, wash the area well with soap and water.
- If you get the granules or prepared oral suspension in your eyes, rinse with plain water.

What should I avoid while taking PROGRAF?

- While you take PROGRAF you should not receive any live vaccines.
- Limit the amount of time you spend in sunlight and avoid exposure to ultraviolet (UV) light, such as tanning machines. Wear protective clothing and use a sunscreen with a high sun protection factor (SPF).
- Do not eat grapefruit or drink grapefruit juice during treatment with PROGRAF.

What are the possible side effects of PROGRAF?

PROGRAF may cause serious side effects, including:

- See “What is the most important information I should know about PROGRAF?”
- problems from medicine errors. People who take PROGRAF have sometimes been given the wrong type of tacrolimus product. Tacrolimus extended-release medicines are not the same as PROGRAF capsules or granules and cannot be substituted for each other. Check your PROGRAF when you get a new prescription and before you take it to make sure you have received PROGRAF capsules or PROGRAF Granules.
- Check with the pharmacist and call your healthcare provider if you think you were given the wrong medicine.
- high blood sugar (diabetes). Your healthcare provider may do blood tests to check for diabetes while you take PROGRAF. Call your healthcare provider right away if you have any symptoms of high blood sugar, including:

- frequent urination
- increased thirst or hunger
- blurred vision
- confusion

- drowsiness
- loss of appetite
- fruity smell on your breath
- nausea, vomiting, or stomach pain

- kidney problems. Kidney problems are a serious and common side effect of PROGRAF. Your healthcare provider may do blood tests to check your kidney function while you take PROGRAF.
- nervous system problems. Nervous system problems are a serious and common side effect of PROGRAF. Call your healthcare provider right away if you get any of these symptoms while taking PROGRAF. These could be signs of a serious nervous system problem:

- headache
- confusion
- seizures
- changes in your vision

- changes in behavior
- coma
- tremors
- numbness and tingling

- high levels of potassium in your blood. Your healthcare provider may do blood tests to check your potassium level while you take PROGRAF.
- high blood pressure. High blood pressure is a serious and common side effect of PROGRAF. Your healthcare provider will monitor your blood pressure while you take PROGRAF and may prescribe blood pressure medicine for you, if needed. Your healthcare provider may instruct you to check your blood pressure at home.
- changes in the electrical activity of your heart (QT prolongation).
- heart problems (myocardial hypertrophy). Tell your healthcare provider right away if you get any of these symptoms of heart problems while taking PROGRAF:

- shortness of breath
- chest pain

- feel lightheaded
- feel faint

- severe low red blood cell count (anemia).
- blood clotting problems: Tell your healthcare provider right away if you have fever and bruising under the skin that may appear as red dots, with or without unexplained tiredness, confusion, yellowing of the skin or eyes, decreased urination. When taken with sirolimus or everolimus, the risk of developing these symptoms may increase.

The most common side effects of PROGRAF in people who have received a kidney, liver, heart, or lung transplant are:

- infections in general, including cytomegalovirus (cmv) infection
- tremors (shaking of the body)
- constipation
- diarrhea
- headache
- stomach pain
- trouble sleeping
- nausea
- high blood sugar (diabetes)
- low levels of magnesium in your blood
- low levels of phosphate in your blood

- swelling of the hands, legs, ankles, or feet
- weakness
- pain
- high levels of fat in your blood
- high levels of potassium in your blood
- low red blood cell count (anemia)
- low white blood cell count
- fever
- numbness or tingling in your hands and feet
- inflammation of your airway (bronchitis)
- fluid around your heart

Tell your healthcare provider if you have any side effect that bothers you or that does not go away.

These are not all the possible side effects of PROGRAF. For more information, ask your healthcare provider or pharmacist.

Call your doctor for medical advice about side effects. You may report side effects to FDA at 1-800-FDA-1088.

How should I store PROGRAF?

PROGRAF capsules

- Store PROGRAF capsules at room temperature between 68°F to 77°F (20°C to 25°C).

PROGRAF Granules

- Store PROGRAF Granules packets at room temperature between 68°F to 77°F (20°C to 25°C).

Keep PROGRAF and all medicines out of the reach of children.

General information about the safe and effective use of PROGRAF.

- Medicines are sometimes prescribed for purposes other than those listed in a Patient Information leaflet. Do not use PROGRAF for a condition for which it was not prescribed. Do not give PROGRAF to other people, even if they have the same symptoms that you have. It may harm them. You can ask your pharmacist or healthcare provider for information about PROGRAF that is written for health professionals.
- This Patient Information leaflet summarizes the most important information about PROGRAF. If you would like more information, talk to your healthcare provider.

What are the ingredients in PROGRAF?

Active ingredient: tacrolimus

Inactive ingredients:

PROGRAF capsules: croscarmellose sodium, hypromellose, lactose monohydrate, and magnesium stearate. The 0.5 mg capsule shell contains ferric oxide, gelatin, and titanium dioxide. The 1 mg capsule shell contains gelatin and titanium dioxide. The 5 mg capsule shell contains ferric oxide, gelatin, and titanium dioxide.

PROGRAF Granules: croscarmellose sodium, hypromellose, and lactose monohydrate.

Distributed by: Astellas Pharma US, Inc. Northbrook, IL 60062

PROGRAF® is a registered trademark of Astellas Pharma Inc. All other trademarks and registered trademarks are the property of their respective owners.

398977-PRG

For more information, go to www.astellas.com/us or call 1-800-727-7003.

This Patient Information has been approved by the U.S. Food and Drug Administration. Revised: 08/2023

Instructions for Use

PROGRAF® Granules
(PRO-graf)
(tacrolimus for oral suspension)

Your healthcare provider has prescribed PROGRAF® Granules, which comes in individual packets that will need to be mixed with water before giving the medicine to your child.

Read this Instructions for Use and the Patient Information for the first time and each time you get a refill of PROGRAF Granules (tacrolimus for oral suspension). There may be new information.

This Instructions for Use does not take the place of talking to your child’s healthcare provider about their medical condition or treatment. Ask the healthcare provider if you have any questions about how to mix or give a dose of PROGRAF Granules the right way.

Important information:
These instructions are for preparing PROGRAF Granules only.
These instructions should not be used for PROGRAF capsules.

- Mix PROGRAF Granules in water to make an oral suspension.
- Give all of the prepared oral suspension to your child right away after preparing. Do not save the prepared oral suspension for later use.
- Use glass or metal materials to prepare your child’s dose of PROGRAF Granules.
  - Do not use any plastic (PVC) materials to prepare PROGRAF Granules. The granules will stick to a plastic container and your child may not receive their full dose.
- Do not breathe in (inhale) or let the granules in PROGRAF or the prepared oral suspension come in contact with your skin or eyes.
  - If you get the granules or the prepared oral suspension on your skin, wash the area well with soap and water.
  - If you get the granules or the prepared oral suspension in your eyes, rinse with plain water.

If you spill the granules, wipe the surface with a wet paper towel. If you spill the prepared oral suspension, dry the area with a dry paper towel and then wipe the area with a wet paper towel. Throw away the paper towels in the trash and wash your hands well with soap and water.

For each dose of PROGRAF Granules mixed with water that will be given using a glass cup, you will need the following supplies (See Figure A):

- Carton containing PROGRAF Granules packets. Follow the instructions on the carton for the number of packets your child’s healthcare provider has prescribed for each dose.
- paper towels
- pair of scissors
- metal stirring spoon
- measuring device
- 1 small clean glass cup (plastic containers should not be used)
- container with drinking water

Figure A

Step 1 | Choose a clean flat work surface. Place a clean paper towel on the work surface. Place the supplies to prepare the dose on the paper towel.
Step 2 | Wash and dry your hands.
Step 3 | Remove the prescribed number of PROGRAF Granules packets from the carton.
Step 4 | Using a pair of scissors, cut along the dotted line on 1 PROGRAF Granules packet to open it.
Step 5 | Empty all of the granules in the packet into the glass cup. Check for any remaining granules in the packet and empty these into the glass cup.
Step 6 | If more than 1 packet of PROGRAF Granules is needed for your child’s prescribed dose, repeat Steps 4 and 5 using the number of packets needed for the prescribed dose.
Step 7 | Add 1 to 2 tablespoons (15 to 30 milliliters) of room temperature drinking water to the glass cup containing the granules.
Step 8 | Gently stir the granules and water in the glass cup with a metal stirring spoon. The granules will not completely dissolve. You will see granules that are suspended in the water.
Step 9 | Give the granules and water suspension in the glass cup to your child. Make sure your child drinks all of the medicine in the cup.; Give all of the medicine to your child right away after preparing. Do not save the medicine for later use.
Step 10 | To make sure all of the medicine is given to your child, refill the glass cup with the same amount of water used in Step 7.
Step 11 | Gently swirl the glass cup to mix any remaining granules.
Step 12 | Give all of the medicine in the cup to the child.
Step 13 | Wash the glass cup. Throw away the paper towel and clean the work surface. Wash your hands.

For each dose of PROGRAF Granules (tacrolimus for oral suspension) mixed with water that will be drawn up and given using an oral syringe, you will need the following supplies (See Figure B):

- Carton containing PROGRAF Granules packets. Follow the instructions on the carton for the number of packets your child’s healthcare provider has prescribed for each dose.
- paper towels
- pair of scissors
- metal stirring spoon
- measuring device
- 1 small clean glass cup (plastic containers should not be used)
- container with drinking water
- 1 non-PVC oral syringe (ask your pharmacist for the oral syringe you should use)

Figure B

Step 1 | Choose a clean flat work surface. Place a clean paper towel on the work surface. Place the supplies to prepare the dose on the paper towel.
Step 2 | Wash and dry your hands.
Step 3 | Remove the prescribed number of PROGRAF Granules packets from the carton.
Step 4 | Using a pair of scissors, cut along the dotted line on 1 PROGRAF Granules packet to open it.
Step 5 | Empty all of the granules in the packet into the glass cup. Check for any remaining granules in the packet and empty these into the glass cup.
Step 6 | If more than 1 packet of PROGRAF Granules is needed for your child’s prescribed dose, repeat Steps 4 and 5 using the number of packets needed for the prescribed dose.
Step 7 | Add 1 to 2 tablespoons (15 to 30 milliliters) of room temperature drinking water to the glass cup containing the granules.
Step 8 | Gently stir the granules and drinking water in the glass cup with a metal stirring spoon. The granules will not completely dissolve. You will see granules that are suspended in the drinking water.
Step 9 | Insert the tip of the oral syringe into the glass cup.; Pull back on the plunger of the oral syringe to draw up the suspension.
Step 10 | Place the tip of the oral syringe in your child’s mouth along the inner cheek. Slowly push the plunger all the way down to give your child all of the medicine in the oral syringe. Repeat Steps 9 and 10 until the glass cup is empty. Give all of the medicine to your child right away after preparing. Do not save the medicine for later use.
Step 11 | To make sure all of the medicine is given to your child, refill the glass cup with the same amount of drinking water used in Step 7.
Step 12 | Gently swirl the glass cup to mix any remaining granules.
Step 13 | Repeat Steps 9 and 10 until the glass cup is empty.
Step 14 | Rinse the plunger and barrel of the syringe well with drinking water and dry well before storing the oral syringe.
Step 15 | Wash the glass cup. Throw away the paper towel and clean the work surface. Wash your hands.

How should I store PROGRAF Granules packets?

Store PROGRAF Granules packets at room temperature between 68°F to 77°F (20°C to 25°C).

Do not throw away any medicines via wastewater or household waste. Ask your pharmacist how to throw away medicines you no longer use.

Keep PROGRAF Granules and all medicine out of the reach of children.

This Instructions for Use has been approved by the U.S. Food and Drug Administration.

Distributed by:
Astellas Pharma US, Inc.
Northbrook, IL 60062

PROGRAF® is a registered trademark of Astellas Pharma Inc.

341124-PRG

Revised: 11/2022

PRINCIPAL DISPLAY PANEL

0.5 mg Individual Carton

PRINCIPAL DISPLAY PANEL

1 mg Individual Carton

PRINCIPAL DISPLAY PANEL

5 mg Individual Carton

PRINCIPAL DISPLAY PANEL

Ampule Carton

PACKAGE/LABEL PRINCIPAL DISPLAY PANEL

0.2 mg Carton

PACKAGE/LABEL PRINCIPAL DISPLAY PANEL

1 mg Carton